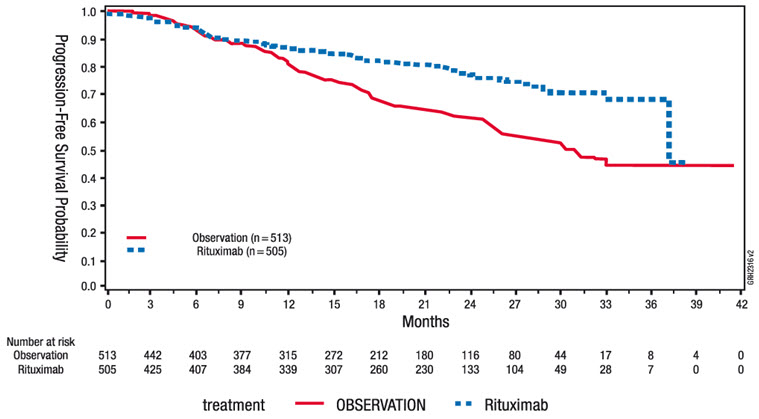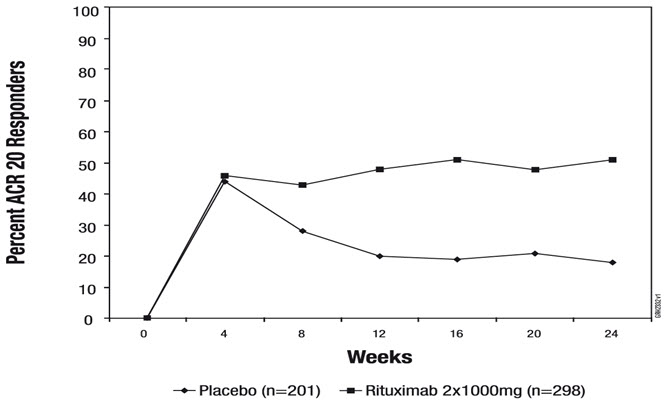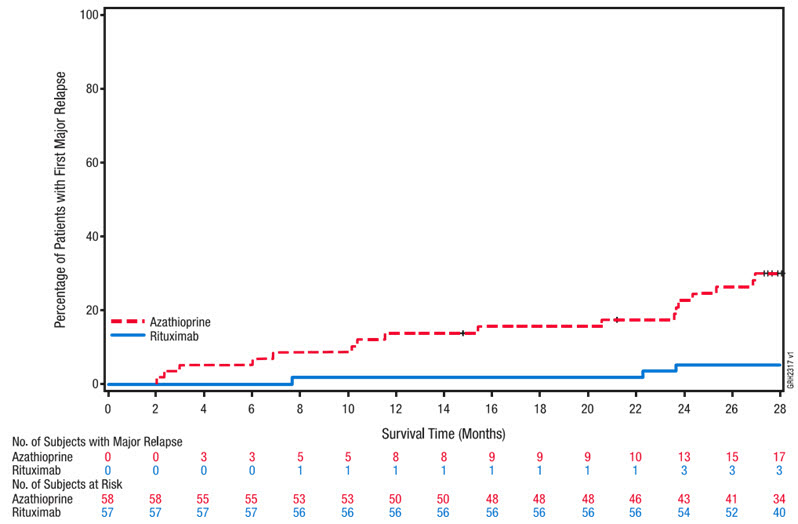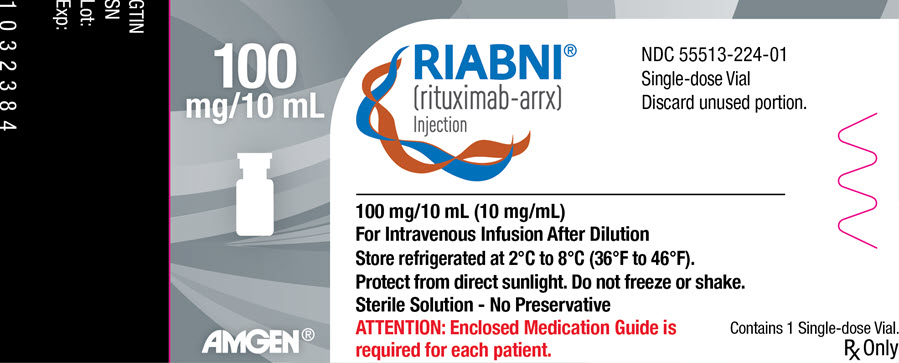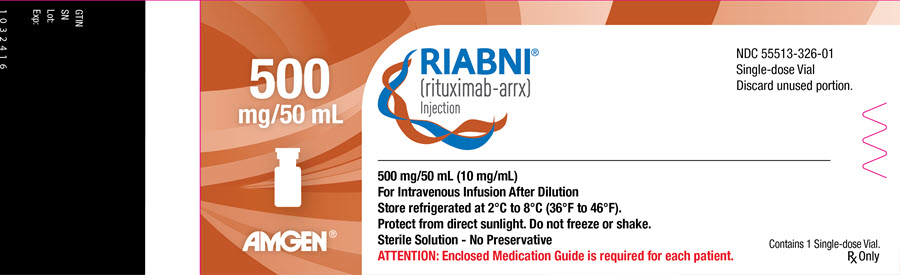 DRUG LABEL: Riabni
NDC: 55513-224 | Form: INJECTION, SOLUTION
Manufacturer: Amgen, Inc
Category: prescription | Type: HUMAN PRESCRIPTION DRUG LABEL
Date: 20250912

ACTIVE INGREDIENTS: RITUXIMAB 100 mg/10 mL
INACTIVE INGREDIENTS: POLYSORBATE 80 7 mg/10 mL; SODIUM CHLORIDE 90 mg/10 mL; TRISODIUM CITRATE DIHYDRATE 73.5 mg/10 mL; WATER

HIGHLIGHTS OF PRESCRIBING INFORMATION

These highlights do not include all the information needed to use RIABNI safely and effectively. See full prescribing information for RIABNI.
RIABNI® (rituximab-arrx) injection, for intravenous use
Initial U.S. Approval: 2020
RIABNI (rituximab-arrx) is biosimilar [Biosimilar means that the biological product is approved based on data demonstrating that it is highly similar to an FDA-approved biological product, known as a reference product, and that there are no clinically meaningful differences between the biosimilar product and the reference product. Biosimilarity of RIABNI has been demonstrated for the condition(s) of use (e.g., indication(s), dosing regimen(s), strength(s), dosage form(s) and route(s) of administration) described in its Full Prescribing Information.] to RITUXAN (rituximab)

WARNING: FATAL INFUSION-RELATED REACTIONS, SEVERE MUCOCUTANEOUS REACTIONS, HEPATITIS B VIRUS REACTIVATION and PROGRESSIVE MULTIFOCAL LEUKOENCEPHALOPATHY

See full prescribing information for complete boxed warning.

- Fatal infusion-related reactions within 24 hours of rituximab infusion; approximately 80% of fatal reactions occurred with first infusion. Monitor patients and discontinue RIABNI infusion for severe reactions (5.1).
- Severe mucocutaneous reactions, some with fatal outcomes (5.2).
- Hepatitis B virus (HBV) reactivation, in some cases resulting in fulminant hepatitis, hepatic failure, and death (5.3).
- Progressive multifocal leukoencephalopathy (PML) resulting in death (5.4).

RECENT MAJOR CHANGES

Indications and Usage, Pemphigus Vulgaris (PV) (1.5) | 6/2025
Dosage and Administration, Recommended Dose for (PV) (2.7) | 6/2025
Dosage and Administration, Recommended Dose for Premedication and Prophylactic Medications (2.8) | 6/2025
Warnings and Precautions, Infusion Related Reactions (5.1) | 6/2025
Warnings and Precautions (5.12) | 6/2025

1 INDICATIONS AND USAGE

RIABNI is a CD20-directed cytolytic antibody indicated for the treatment of:

- Adult patients with Non-Hodgkin's Lymphoma (NHL) (1.1).
  - Relapsed or refractory, low grade or follicular, CD20-positive B-cell NHL as a single agent.
  - Previously untreated follicular, CD20-positive, B-cell NHL in combination with first line chemotherapy and, in patients achieving a complete or partial response to a rituximab product in combination with chemotherapy, as single-agent maintenance therapy.
  - Non-progressing (including stable disease), low-grade, CD20-positive, B-cell NHL as a single agent after first-line cyclophosphamide, vincristine, and prednisone (CVP) chemotherapy.
  - Previously untreated diffuse large B-cell, CD20-positive NHL in combination with cyclophosphamide, doxorubicin, vincristine, and prednisone (CHOP) or other anthracycline-based chemotherapy regimens.
- Adult patients with Chronic Lymphocytic Leukemia (CLL) (1.2).
  - Previously untreated and previously treated CD20-positive CLL in combination with fludarabine and cyclophosphamide (FC).
- Rheumatoid Arthritis (RA) in combination with methotrexate in adult patients with moderately- to-severely- active RA who have inadequate response to one or more TNF antagonist therapies (1.3).
- Granulomatosis with Polyangiitis (GPA) (Wegener's Granulomatosis) and Microscopic Polyangiitis (MPA) in adult patients in combination with glucocorticoids (1.4).
- Moderate to severe Pemphigus Vulgaris (PV) in adult patients (1.5).

2 DOSAGE AND ADMINISTRATION

- Administer only as an intravenous infusion (2.1).
- Do not administer as an intravenous push or bolus (2.1).
- RIABNI should only be administered by a healthcare professional with appropriate medical support to manage severe infusion-related reactions that can be fatal if they occur (2.1).
- The dose for adult B-cell NHL is 375 mg/m^2 (2.2).
- The dose for CLL is 375 mg/m^2 in the first cycle and 500 mg/m^2 in cycles 2–6, in combination with FC, administered every 28 days (2.3).
- The dose as a component of Zevalin® (ibritumomab tiuxetan) Therapeutic Regimen is 250 mg/m^2 (2.4).
- The dose for RA in combination with methotrexate is two-1,000 mg intravenous infusions separated by 2 weeks (one course) every 24 weeks or based on clinical evaluation, but not sooner than every 16 weeks. Methylprednisolone 100 mg intravenous or equivalent glucocorticoid is recommended 30 minutes prior to each infusion (2.5).
- The induction dose for adult patients with active GPA and MPA in combination with glucocorticoids is 375 mg/m^2 once weekly for 4 weeks. The follow up dose for adult patients with GPA and MPA who have achieved disease control with induction treatment, in combination with glucocorticoids is two 500 mg intravenous infusions separated by two weeks, followed by a 500 mg intravenous infusion every 6 months thereafter based on clinical evaluation (2.6).
- The dose for PV is two-1,000 mg intravenous infusions separated by 2 weeks in combination with a tapering course of glucocorticoids, then a 500 mg intravenous infusion at Month 12 and every 6 months thereafter or based on clinical evaluation. Dose upon relapse is a 1,000 mg intravenous infusion with considerations to resume or increase the glucocorticoid dose based on clinical evaluation. Subsequent infusions may be no sooner than 16 weeks after the previous infusion (2.7). Methylprednisolone 100 mg intravenous or equivalent glucocorticoid is recommended 30 minutes prior to each infusion (2.8).

3 DOSAGE FORMS AND STRENGTHS

- Injection: 100 mg/10 mL (10 mg/mL) and 500 mg/50 mL (10 mg/mL) solution in single-dose vials (3)

4 CONTRAINDICATIONS

None (4)

5 WARNINGS AND PRECAUTIONS

- Tumor lysis syndrome: Administer aggressive intravenous hydration, anti-hyperuricemic agents, monitor renal function (5.5).
- Infections: Withhold RIABNI and institute appropriate anti-infective therapy (5.6).
- Cardiac adverse reactions: Discontinue infusions in case of serious or life-threatening events (5.7).
- Renal toxicity: Discontinue in patients with rising serum creatinine or oliguria (5.8).
- Bowel obstruction and perforation: Consider and evaluate for abdominal pain, vomiting, or related symptoms (5.9).
- Immunizations: Live virus vaccinations prior to or during RIABNI treatment is not recommended (5.10).
- Embryo-Fetal toxicity: Can cause fetal harm. Advise females of reproductive potential of the potential risk to a fetus and use of effective contraception (5.11).

6 ADVERSE REACTIONS

Most common adverse reactions in clinical trials were:

- NHL (greater than or equal to 25%): infusion-related reactions, fever, lymphopenia, chills, infection, and asthenia (6.1).
- CLL (greater than or equal to 25%): infusion-related reactions and neutropenia (6.1).
- RA (greater than or equal to 10%): upper respiratory tract infection, nasopharyngitis, urinary tract infection, and bronchitis (other important adverse reactions include infusion-related reactions, serious infections, and cardiovascular events) (6.1).
- GPA and MPA (greater than or equal to 15%): infections, nausea, diarrhea, headache, muscle spasms, anemia, peripheral edema, infusion-related reactions (6.1).
- PV (greater than or equal to 15%): infusion-related reactions, depression, upper respiratory tract infection/ nasopharyngitis, headache (other important adverse reactions include infections) (6.1).

To report SUSPECTED ADVERSE REACTIONS, contact Amgen, Inc. at 1-800-77-AMGEN (1-800-772-6436) or FDA at 1-800-FDA-1088 or www.fda.gov/medwatch.

7 DRUG INTERACTIONS

Renal toxicity when used in combination with cisplatin (5.8).

8 USE IN SPECIFIC POPULATIONS

- Lactation: Advise not to breastfeed (8.2).
- Geriatric Use: In CLL patients older than 70 years of age, exploratory analyses suggest no benefit with the addition of rituximab to FC (8.5).

FULL PRESCRIBING INFORMATION

WARNING: FATAL INFUSION-RELATED REACTIONS, SEVERE MUCOCUTANEOUS REACTIONS, HEPATITIS B VIRUS REACTIVATION and PROGRESSIVE MULTIFOCAL LEUKOENCEPHALOPATHY

Infusion-Related Reactions

Administration of rituximab products can result in serious, including fatal, infusion-related reactions. Deaths within 24 hours of rituximab infusion have occurred. Approximately 80% of fatal infusion-related reactions occurred in association with the first infusion. Monitor patients closely. Discontinue RIABNI infusion for severe reactions and provide medical treatment for Grade 3 or 4 infusion-related reactions [see Warnings and Precautions (5.1), Adverse Reactions (6.1)].

Severe Mucocutaneous Reactions

Severe, including fatal, mucocutaneous reactions can occur in patients receiving rituximab products [see Warnings and Precautions (5.2)].

Hepatitis B Virus (HBV) Reactivation

HBV reactivation can occur in patients treated with rituximab products, in some cases resulting in fulminant hepatitis, hepatic failure, and death. Screen all patients for HBV infection before treatment initiation and monitor patients during and after treatment with RIABNI. Discontinue RIABNI and concomitant medications in the event of HBV reactivation [see Warnings and Precautions (5.3)].

Progressive Multifocal Leukoencephalopathy (PML), including fatal PML, can occur in patients receiving rituximab products [see Warnings and Precautions (5.4) and Adverse Reactions (6.1)].

1 INDICATIONS AND USAGE

1.1 Non-Hodgkin's Lymphoma (NHL)

RIABNI is indicated for the treatment of adult patients with:

- Relapsed or refractory, low-grade or follicular, CD20-positive, B-cell NHL as a single agent.
- Previously untreated follicular, CD20-positive, B-cell NHL in combination with first line chemotherapy and, in patients achieving a complete or partial response to a rituximab product in combination with chemotherapy, as single-agent maintenance therapy.
- Non-progressing (including stable disease), low-grade, CD20-positive, B-cell NHL as a single agent after first-line cyclophosphamide, vincristine, and prednisone (CVP) chemotherapy.
- Previously untreated diffuse large B-cell, CD20-positive NHL in combination with cyclophosphamide, doxorubicin, vincristine, prednisone (CHOP) or other anthracycline-based chemotherapy regimens.

1.2 Chronic Lymphocytic Leukemia (CLL)

RIABNI, in combination with fludarabine and cyclophosphamide (FC), is indicated for the treatment of adult patients with previously untreated and previously treated CD20-positive CLL.

1.3 Rheumatoid Arthritis (RA)

RIABNI, in combination with methotrexate, is indicated for the treatment of adult patients with moderately- to-severely- active rheumatoid arthritis who have had an inadequate response to one or more TNF antagonist therapies.

1.4 Granulomatosis with Polyangiitis (GPA) (Wegener's Granulomatosis) and Microscopic Polyangiitis (MPA)

RIABNI, in combination with glucocorticoids, is indicated for the treatment of adult patients with Granulomatosis with Polyangiitis (GPA) (Wegener's Granulomatosis) and Microscopic Polyangiitis (MPA).

1.5 Pemphigus Vulgaris (PV)

RIABNI is indicated for the treatment of adult patients with moderate to severe pemphigus vulgaris.

2 DOSAGE AND ADMINISTRATION

2.1 Important Dosing Information

Administer only as an intravenous infusion [see Dosage and Administration (2.8)]. Do not administer as an intravenous push or bolus. RIABNI should only be administered by a healthcare professional with appropriate medical support to manage severe infusion-related reactions that can be fatal if they occur [see Warnings and Precautions (5.1)].

Premedicate before each infusion [see Dosage and Administration (2.8)].

Prior to First Infusion

Screen all patients for HBV infection by measuring HBsAg and anti-HBc before initiating treatment with RIABNI [see Warnings and Precautions (5.3)]. Obtain complete blood counts (CBC) including platelets prior to the first dose.

During RIABNI Therapy

In patients with lymphoid malignancies during treatment with RIABNI monotherapy, obtain complete blood counts (CBC) with differential and platelet counts prior to each RIABNI course. During treatment with RIABNI and chemotherapy, obtain CBC with differential and platelet counts at weekly to monthly intervals and more frequently in patients who develop cytopenias [see Adverse Reactions (6.1)].

In patients with RA, GPA or MPA, obtain CBC with differential and platelet counts at two to four month intervals during RIABNI therapy. Continue to monitor for cytopenias after final dose and until resolution.

- First Infusion:
  Standard Infusion: Initiate infusion at a rate of 50 mg/hour. In the absence of infusion toxicity, increase infusion rate by 50 mg/hour increments every 30 minutes, to a maximum of 400 mg/hour.
- Subsequent Infusions:
  Standard Infusion: Initiate infusion at a rate of 100 mg/hour. In the absence of infusion toxicity, increase rate by 100 mg/hour increments at 30-minute intervals, to a maximum of 400 mg/hour.
  For Previously Untreated Follicular NHL and DLBCL Adult Patients:
  If patients did not experience a Grade 3 or 4 infusion-related adverse event during Cycle 1, a 90-minute infusion can be administered in Cycle 2 with a glucocorticoid-containing chemotherapy regimen.
  Initiate at a rate of 20% of the total dose given in the first 30 minutes and the remaining 80% of the total dose given over the next 60 minutes. If the 90-minute infusion is tolerated in Cycle 2, the same rate can be used when administering the remainder of the treatment regimen (through Cycle 6 or 8).
  Patients who have clinically significant cardiovascular disease or who have a circulating lymphocyte count greater than or equal to 5,000/mm^3 before Cycle 2 should not be administered the 90-minute infusion [see Clinical Studies (14.4)].
- Interrupt the infusion or slow the infusion rate for infusion-related reactions [see Boxed Warning, Warnings and Precautions (5.1)]. Continue the infusion at one-half the previous rate upon improvement of symptoms.

2.2 Recommended Dose for Non-Hodgkin's Lymphoma (NHL)

The recommended dose is 375 mg/m^2 as an intravenous infusion according to the following schedules:

- Relapsed or Refractory, Low-Grade or Follicular, CD20-Positive, B-Cell NHL
  Administer once weekly for 4 or 8 doses.
- Retreatment for Relapsed or Refractory, Low-Grade or Follicular, CD20-Positive, B-Cell NHL
  Administer once weekly for 4 doses.
- Previously Untreated, Follicular, CD20-Positive, B-Cell NHL
  Administer on Day 1 of each cycle of chemotherapy, for up to 8 doses. In patients with complete or partial response, initiate RIABNI maintenance eight weeks following completion of a rituximab product in combination with chemotherapy. Administer RIABNI as a single-agent every 8 weeks for 12 doses.
- Non-progressing, Low-Grade, CD20-Positive, B-Cell NHL, after first-line CVP chemotherapy
  Following completion of 6–8 cycles of CVP chemotherapy, administer once weekly for 4 doses at 6-month intervals to a maximum of 16 doses.
- Diffuse Large B-Cell NHL
  Administer on Day 1 of each cycle of chemotherapy for up to 8 infusions.

2.3 Recommended Dose for Chronic Lymphocytic Leukemia (CLL)

The recommended dose is 375 mg/m^2 the day prior to the initiation of FC chemotherapy, then 500 mg/m^2 on Day 1 of cycles 2–6 (every 28 days).

2.4 Recommended Dose as a Component of Zevalin® for Treatment of NHL

When used as part of the Zevalin therapeutic regimen, infuse 250 mg/m^2 in accordance with the Zevalin package insert. Refer to the Zevalin package insert for full prescribing information regarding the Zevalin therapeutic regimen.

2.5 Recommended Dose for Rheumatoid Arthritis (RA)

- Administer RIABNI as two-1,000 mg intravenous infusions separated by 2 weeks.
- Glucocorticoids administered as methylprednisolone 100 mg intravenous or its equivalent 30 minutes prior to each infusion are recommended to reduce the incidence and severity of infusion-related reactions.
- Subsequent courses should be administered every 24 weeks or based on clinical evaluation, but not sooner than every 16 weeks.
- RIABNI is given in combination with methotrexate.

2.6 Recommended Dose for Granulomatosis with Polyangiitis (GPA) (Wegener's Granulomatosis) and Microscopic Polyangiitis (MPA)

Induction Treatment of Adult Patients with Active GPA/MPA

- Administer RIABNI as a 375 mg/m^2 intravenous infusion once weekly for 4 weeks for patients with active GPA or MPA.
- Glucocorticoids administered as methylprednisolone 1,000 mg intravenously per day for 1 to 3 days followed by oral prednisone as per clinical practice. This regimen should begin within 14 days prior to or with the initiation of RIABNI and may continue during and after the 4 week induction course of RIABNI treatment.

Follow up Treatment of Adult Patients with GPA/MPA who have Achieved Disease Control with Induction Treatment

- Administer RIABNI as two 500 mg intravenous infusions separated by two weeks, followed by a 500 mg intravenous infusion every 6 months thereafter based on clinical evaluation.
- If induction treatment of active disease was with a rituximab product, initiate follow up treatment with RIABNI within 24 weeks after the last induction infusion with a rituximab product or based on clinical evaluation, but no sooner than 16 weeks after the last induction infusion with a rituximab product.
- If induction treatment of active disease was with other standard of care immunosuppressants, initiate RIABNI follow up treatment within the 4 week period that follows achievement of disease control.

2.7 Recommended Dose for Pemphigus Vulgaris (PV)

- Administer RIABNI as two-1,000 mg intravenous infusions separated by 2 weeks in combination with a tapering course of glucocorticoids.
- Maintenance treatment
  Administer RIABNI as a 500 mg intravenous infusion at Month 12 and every 6 months thereafter or based on clinical evaluation.
- Treatment of relapse
  Administer RIABNI as a 1,000 mg intravenous infusion on relapse, and consider resuming or increasing the glucocorticoid dose based on clinical evaluation.

Subsequent infusions of RIABNI may be administered no sooner than 16 weeks following the previous infusion.

2.8 Recommended Dose for Premedication and Prophylactic Medications

Premedicate with acetaminophen and an antihistamine before each infusion of RIABNI. For adult patients administered RIABNI according to the 90-minute infusion rate, the glucocorticoid component of their chemotherapy regimen should be administered prior to infusion [see Clinical Studies (14.4)].

For RA, GPA and MPA, and PV patients, methylprednisolone 100 mg intravenously or its equivalent is recommended 30 minutes prior to each infusion. Provide prophylaxis treatment for Pneumocystis jirovecii pneumonia (PCP) and herpes virus infections for patients with CLL during treatment and for up to 12 months following treatment as appropriate [see Warnings and Precautions (5.6)].

PCP prophylaxis is also recommended for patients with GPA and MPA during treatment and for at least 6 months following the last RIABNI infusion.

PCP prophylaxis should be considered for patients with PV during and following RIABNI treatment.

2.9 Administration and Storage

Use appropriate aseptic technique. Parenteral drug products should be inspected visually for particulate matter and discoloration prior to administration. RIABNI should be a clear to slightly opalescent, colorless to slightly yellow liquid. Do not use vial if particulates or discoloration is present.

Administration

Use a sterile needle and syringe to prepare RIABNI. Withdraw the necessary amount of RIABNI and dilute to a final concentration of 1 mg/mL to 4 mg/mL in an infusion bag containing either 0.9% Sodium Chloride Injection, USP, or 5% Dextrose Injection, USP. Gently invert the bag to mix the solution. Do not mix or dilute with other drugs. Discard any unused portion left in the vial.

Storage

If not used immediately, store diluted RIABNI solutions as shown in Table 1.

Table 1. Diluted RIABNI Solution Storage Conditions
Diluent Used to Prepare Solution for Infusion | Diluted RIABNI Solution Storage Conditions
0.9% Sodium Chloride Injection, USP | Store RIABNI solution diluted in 0.9% Sodium Chloride Injection, USP refrigerated at 2°C to 8°C (36°F to 46°F) for up to 7 days after preparation and protect from light.
5% Dextrose Injection, USP | Store RIABNI solution diluted in 5% Dextrose Injection, USP refrigerated at 2°C to 8°C (36°F to 46°F) for up to 24 hours after preparation.

No incompatibilities between RIABNI and polyvinylchloride or polyethylene bags have been observed.

3 DOSAGE FORMS AND STRENGTHS

Injection: 100 mg/10 mL (10 mg/mL) and 500 mg/50 mL (10 mg/mL) as a clear to slightly opalescent, colorless to slightly yellow solution in a single-dose vial.

4 CONTRAINDICATIONS

None.

5 WARNINGS AND PRECAUTIONS

5.1 Infusion-Related Reactions

Rituximab products can cause severe, including fatal, infusion-related reactions. Severe reactions typically occurred during the first infusion with time to onset of 30–120 minutes. Rituximab product-induced infusion-related reactions and sequelae include urticaria, hypotension, angioedema, hypoxia, bronchospasm, pulmonary infiltrates, acute respiratory distress syndrome, myocardial infarction, ventricular fibrillation, cardiogenic shock, anaphylactoid events, or death.

Premedicate patients with an antihistamine and acetaminophen prior to dosing. For RA, GPA and MPA, and PV patients, methylprednisolone 100 mg intravenously or its equivalent is recommended 30 minutes prior to each infusion. Institute medical management (e.g., glucocorticoids, epinephrine, bronchodilators, or oxygen) for infusion-related reactions as needed. Depending on the severity of the infusion-related reaction and the required interventions, temporarily or permanently discontinue RIABNI. Resume infusion at a minimum 50% reduction in rate after symptoms have resolved. Closely monitor the following patients: those with pre-existing cardiac or pulmonary conditions, those who experienced prior cardiopulmonary adverse reactions, and those with high numbers of circulating malignant cells (greater than or equal to 25,000/mm^3) [see Warnings and Precautions (5.7), Adverse Reactions (6.1)].

5.2 Severe Mucocutaneous Reactions

Mucocutaneous reactions, some with fatal outcome, can occur in patients treated with rituximab products. These reactions include paraneoplastic pemphigus, Stevens-Johnson syndrome, lichenoid dermatitis, vesiculobullous dermatitis, and toxic epidermal necrolysis. The onset of these reactions has been variable and includes reports with onset on the first day of rituximab exposure. Discontinue RIABNI in patients who experience a severe mucocutaneous reaction. The safety of re-administration of rituximab products to patients with severe mucocutaneous reactions has not been determined.

5.3 Hepatitis B Virus (HBV) Reactivation

Hepatitis B virus (HBV) reactivation, in some cases resulting in fulminant hepatitis, hepatic failure and death, can occur in patients treated with drugs classified as CD20-directed cytolytic antibodies, including rituximab products. Cases have been reported in patients who are hepatitis B surface antigen (HBsAg) positive and also in patients who are HBsAg negative but are hepatitis B core antibody (anti-HBc) positive. Reactivation also has occurred in patients who appear to have resolved hepatitis B infection (i.e., HBsAg negative, anti-HBc positive and hepatitis B surface antibody [anti-HBs] positive).

HBV reactivation is defined as an abrupt increase in HBV replication manifesting as a rapid increase in serum HBV DNA levels or detection of HBsAg in a person who was previously HBsAg negative and anti-HBc positive. Reactivation of HBV replication is often followed by hepatitis, i.e., increase in transaminase levels. In severe cases increase in bilirubin levels, liver failure, and death can occur.

Screen all patients for HBV infection by measuring HBsAg and anti-HBc before initiating treatment with RIABNI. For patients who show evidence of prior hepatitis B infection (HBsAg positive [regardless of antibody status] or HBsAg negative but anti-HBc positive), consult with physicians with expertise in managing hepatitis B regarding monitoring and consideration for HBV antiviral therapy before and/or during RIABNI treatment.

Monitor patients with evidence of current or prior HBV infection for clinical and laboratory signs of hepatitis or HBV reactivation during and for several months following RIABNI therapy. HBV reactivation has been reported up to 24 months following completion of rituximab therapy.

In patients who develop reactivation of HBV while on RIABNI, immediately discontinue RIABNI and any concomitant chemotherapy, and institute appropriate treatment. Insufficient data exist regarding the safety of resuming RIABNI treatment in patients who develop HBV reactivation. Resumption of RIABNI treatment in patients whose HBV reactivation resolves should be discussed with physicians with expertise in managing HBV.

5.4 Progressive Multifocal Leukoencephalopathy (PML)

JC virus infection resulting in PML and death can occur in rituximab product-treated patients with hematologic malignancies or with autoimmune diseases. The majority of patients with hematologic malignancies diagnosed with PML received rituximab in combination with chemotherapy or as part of a hematopoietic stem cell transplant. The patients with autoimmune diseases had prior or concurrent immunosuppressive therapy. Most cases of PML were diagnosed within 12 months of their last infusion of rituximab.

Consider the diagnosis of PML in any patient presenting with new-onset neurologic manifestations. Evaluation of PML includes, but is not limited to, consultation with a neurologist, brain MRI, and lumbar puncture.

Discontinue RIABNI and consider discontinuation or reduction of any concomitant chemotherapy or immunosuppressive therapy in patients who develop PML.

5.5 Tumor Lysis Syndrome (TLS)

Acute renal failure, hyperkalemia, hypocalcemia, hyperuricemia, or hyperphosphatemia from tumor lysis, sometimes fatal, can occur within 12–24 hours after the first infusion of rituximab products in patients with NHL. A high number of circulating malignant cells (greater than or equal to 25,000/mm^3) or high tumor burden, confers a greater risk of TLS.

Administer aggressive intravenous hydration and anti-hyperuricemic therapy in patients at high risk for TLS. Correct electrolyte abnormalities, monitor renal function and fluid balance, and administer supportive care, including dialysis as indicated [see Warnings and Precautions (5.8)].

5.6 Infections

Serious, including fatal, bacterial, fungal, and new or reactivated viral infections can occur during and following the completion of rituximab product-based therapy. Infections have been reported in some patients with prolonged hypogammaglobulinemia (defined as hypogammaglobulinemia greater than 11 months after rituximab exposure). New or reactivated viral infections included cytomegalovirus, herpes simplex virus, parvovirus B19, varicella zoster virus, West Nile virus, and hepatitis B and C. Discontinue RIABNI for serious infections and institute appropriate anti-infective therapy [see Adverse Reactions (6.1, 6.3)]. RIABNI is not recommended for use in patients with severe, active infections.

5.7 Cardiovascular Adverse Reactions

Cardiac adverse reactions, including ventricular fibrillation, myocardial infarction, and cardiogenic shock may occur in patients receiving rituximab products. Discontinue infusions for serious or life-threatening cardiac arrhythmias. Perform cardiac monitoring during and after all infusions of RIABNI for patients who develop clinically significant arrhythmias, or who have a history of arrhythmia or angina [see Adverse Reactions (6.1)].

5.8 Renal Toxicity

Severe, including fatal, renal toxicity can occur after rituximab product administration in patients with NHL. Renal toxicity has occurred in patients who experience tumor lysis syndrome and in patients with NHL administered concomitant cisplatin therapy during clinical trials. The combination of cisplatin and RIABNI is not an approved treatment regimen. Monitor closely for signs of renal failure and discontinue RIABNI in patients with a rising serum creatinine or oliguria [see Warnings and Precautions (5.5)].

5.9 Bowel Obstruction and Perforation

Abdominal pain, bowel obstruction and perforation, in some cases leading to death, can occur in patients receiving rituximab products in combination with chemotherapy. In postmarketing reports, the mean time to documented gastrointestinal perforation was 6 (range 1–77) days in patients with NHL. Evaluate if symptoms of obstruction such as abdominal pain or repeated vomiting occur.

5.10 Immunization

The safety of immunization with live viral vaccines following rituximab product therapy has not been studied and vaccination with live virus vaccines is not recommended before or during treatment.

For patients treated with RIABNI, physicians should review the patient's vaccination status and patients should, if possible, be brought up-to-date with all immunizations in agreement with current immunization guidelines prior to initiating RIABNI and administer non-live vaccines at least 4 weeks prior to a course of RIABNI.

The effect of rituximab on immune responses was assessed in a randomized, controlled study in patients with RA treated with rituximab and methotrexate (MTX) compared to patients treated with MTX alone. A response to pneumococcal vaccination (a T-cell independent antigen) as measured by an increase in antibody titers to at least 6 of 12 serotypes was lower in patients treated with rituximab plus MTX as compared to patients treated with MTX alone (19% vs. 61%). A lower proportion of patients in the rituximab plus MTX group developed detectable levels of anti-keyhole limpet hemocyanin antibodies (a novel protein antigen) after vaccination compared to patients on MTX alone (47% vs. 93%).

A positive response to tetanus toxoid vaccine (a T-cell dependent antigen with existing immunity) was similar in patients treated with rituximab plus MTX compared to patients on MTX alone (39% vs. 42%). The proportion of patients maintaining a positive Candida skin test (to evaluate delayed type hypersensitivity) was also similar (77% of patients on rituximab plus MTX vs. 70% of patients on MTX alone).

Most patients in the rituximab-treated group had B-cell counts below the lower limit of normal at the time of immunization. The clinical implications of these findings are not known.

5.11 Embryo-Fetal Toxicity

Based on human data, rituximab products can cause fetal harm due to B-cell lymphocytopenia in infants exposed in utero. Advise pregnant women of the potential risk to a fetus. Advise females of reproductive potential to use effective contraception while receiving RIABNI and for 12 months after the last dose [see Use in Specific Populations (8.1, 8.3)].

5.12 Concomitant Use with Other Biologic Agents and DMARDS other than Methotrexate in RA, GPA and MPA, PV

Limited data are available on the safety of the use of biologic agents or disease modifying antirheumatic drugs (DMARDs) other than methotrexate in RA patients exhibiting peripheral B-cell depletion following treatment with rituximab. Observe patients closely for signs of infection if biologic agents and/or DMARDs are used concomitantly. Use of concomitant immunosuppressants other than corticosteroids has not been studied in GPA or MPA or PV patients exhibiting peripheral B-cell depletion following treatment with rituximab products.

5.13 Use in RA Patients Who Have Not Had Prior Inadequate Response to Tumor Necrosis Factor (TNF) Antagonists

While the efficacy of rituximab was supported in four controlled trials in patients with RA with prior inadequate responses to non-biologic DMARDs, and in a controlled trial in MTX-naïve patients, a favorable risk-benefit relationship has not been established in these populations. The use of RIABNI in patients with RA who have not had prior inadequate response to one or more TNF antagonists is not recommended [see Clinical Studies (14.6)].

6 ADVERSE REACTIONS

The following clinically significant adverse reactions are discussed in greater detail in other sections of the labeling:

- Infusion-related reactions [see Warnings and Precautions (5.1)]
- Severe mucocutaneous reactions [see Warnings and Precautions (5.2)]
- Hepatitis B reactivation with fulminant hepatitis [see Warnings and Precautions (5.3)]
- Progressive multifocal leukoencephalopathy [see Warnings and Precautions (5.4)]
- Tumor lysis syndrome [see Warnings and Precautions (5.5)]
- Infections [see Warnings and Precautions (5.6)]
- Cardiovascular adverse reactions [see Warnings and Precautions (5.7)]
- Renal toxicity [see Warnings and Precautions (5.8)]
- Bowel obstruction and perforation [see Warnings and Precautions (5.9)]

6.1 Clinical Trials Experience

Because clinical trials are conducted under widely varying conditions, adverse reaction rates observed in the clinical trials of a drug cannot be directly compared to rates in the clinical trials of another drug and may not reflect the rates observed in clinical practice.

B-Cell Malignancies

The data described below reflect exposure to rituximab in 3,092 patients, with exposures ranging from a single infusion up to 2 years. Rituximab was studied in both single-arm and controlled trials (n = 356 and n = 2,427). The population included 1,180 patients with low grade or follicular lymphoma, 927 patients with DLBCL, 676 patients with CLL, and 309 patients with another indication. Most NHL patients received rituximab as an infusion of 375 mg/m^2 per infusion, given as a single agent weekly for up to 8 doses, in combination with chemotherapy for up to 8 doses, or following chemotherapy for up to 16 doses.

CLL patients received rituximab 375 mg/m^2 as an initial infusion followed by 500 mg/m^2 for up to 5 doses, in combination with fludarabine and cyclophosphamide. Seventy-one percent of CLL patients received 6 cycles and 90% received at least 3 cycles of rituximab-based therapy.

The most common adverse reactions of rituximab (incidence greater than or equal to 25%) observed in clinical trials of patients with NHL were infusion-related reactions, fever, lymphopenia, chills, infection, and asthenia.

The most common adverse reactions of rituximab (incidence greater than or equal to 25%) observed in clinical trials of patients with CLL were: infusion-related reactions and neutropenia.

Infusion-Related Reactions

In the majority of patients with NHL, infusion-related reactions consisting of fever, chills/rigors, nausea, pruritus, angioedema, hypotension, headache, bronchospasm, urticaria, rash, vomiting, myalgia, dizziness, or hypertension occurred during the first rituximab infusion. Infusion-related reactions typically occurred within 30 to 120 minutes of beginning the first infusion and resolved with slowing or interruption of the rituximab infusion and with supportive care (diphenhydramine, acetaminophen, and intravenous saline). The incidence of infusion-related reactions was highest during the first infusion (77%) and decreased with each subsequent infusion [see Warnings and Precautions (5.1)]. In adult patients with previously untreated follicular NHL or previously untreated DLBCL, who did not experience a Grade 3 or 4 infusion-related reaction in Cycle 1 and received a 90-minute infusion of rituximab at Cycle 2, the incidence of Grade 3-4 infusion-related reactions on the day of, or day after the infusion was 1.1% (95% CI [0.3%, 2.8%]). For Cycles 2-8, the incidence of Grade 3-4 infusion-related reactions on the day of or day after the 90-minute infusion, was 2.8% (95% CI [1.3%, 5.0%]) [see Warnings and Precautions (5.1), Clinical Studies (14.4)].

Infections

Serious infections (NCI-CTCAE Grade 3 or 4), including sepsis, occurred in less than 5% of patients with NHL in the single-arm studies. The overall incidence of infections was 31% (bacterial 19%, viral 10%, unknown 6%, and fungal 1%) [see Warnings and Precautions (5.6)].

In randomized, controlled studies where rituximab was administered following chemotherapy for the treatment of follicular or low-grade NHL, the rate of infection was higher among patients who received rituximab. In diffuse large B-cell lymphoma patients, viral infections occurred more frequently in those who received rituximab.

Cytopenias and Hypogammaglobulinemia

In patients with NHL receiving rituximab monotherapy, NCI-CTC Grade 3 and 4 cytopenias were reported in 48% of patients. These included lymphopenia (40%), neutropenia (6%), leukopenia (4%), anemia (3%), and thrombocytopenia (2%). The median duration of lymphopenia was 14 days (range, 1–588 days) and of neutropenia was 13 days (range, 2–116 days). A single occurrence of transient aplastic anemia (pure red cell aplasia) and two occurrences of hemolytic anemia following rituximab therapy occurred during the single-arm studies.

In studies of monotherapy, rituximab-induced B-cell depletion occurred in 70% to 80% of patients with NHL. Decreased IgM and IgG serum levels occurred in 14% of these patients.

In CLL trials, the frequency of prolonged neutropenia and late-onset neutropenia was higher in patients treated with rituximab in combination with fludarabine and cyclophosphamide (R-FC) compared to patients treated with FC. Prolonged neutropenia is defined as Grade 3-4 neutropenia that has not resolved between 24 and 42 days after the last dose of study treatment. Late-onset neutropenia is defined as Grade 3-4 neutropenia starting at least 42 days after the last treatment dose.

In patients with previously untreated CLL, the frequency of prolonged neutropenia was 8.5% for patients who received R-FC (n = 402) and 5.8% for patients who received FC (n = 398). In patients who did not have prolonged neutropenia, the frequency of late-onset neutropenia was 14.8% of 209 patients who received R-FC and 4.3% of 230 patients who received FC.

For patients with previously treated CLL, the frequency of prolonged neutropenia was 24.8% for patients who received R-FC (n = 274) and 19.1% for patients who received FC (n = 274). In patients who did not have prolonged neutropenia, the frequency of late-onset neutropenia was 38.7% in 160 patients who received R-FC and 13.6% of 147 patients who received FC.

Relapsed or Refractory, Low-Grade NHL

Adverse reactions presented in Table 2 occurred in 356 patients with relapsed or refractory, low-grade or follicular, CD20-positive, B-cell NHL treated in single-arm studies of rituximab administered as a single agent [see Clinical Studies (14.1)]. Most patients received rituximab 375 mg/m^2 weekly for 4 doses.

Table 2. Incidence of Adverse Reactions in Greater Than or Equal to 5% of Patients with Relapsed or Refractory, Low-Grade or Follicular NHL, Receiving Single-agent Rituximab (N=356) [Adverse reactions observed up to 12 months following rituximab] , [Adverse reactions graded for severity by NCI-CTC criteria]
 | All Grades (%) | Grade 3 and 4 (%)
Any Adverse Reactions | 99 | 57
Body as a Whole | 86 | 10
Fever | 53 | 1
Chills | 33 | 3
Infection | 31 | 4
Asthenia | 26 | 1
Headache | 19 | 1
Abdominal Pain | 14 | 1
Pain | 12 | 1
Back Pain | 10 | 1
Throat Irritation | 9 | 0
Flushing | 5 | 0
Heme and Lymphatic System | 67 | 48
Lymphopenia | 48 | 40
Leukopenia | 14 | 4
Neutropenia | 14 | 6
Thrombocytopenia | 12 | 2
Anemia | 8 | 3
Skin and Appendages | 44 | 2
Night Sweats | 15 | 1
Rash | 15 | 1
Pruritus | 14 | 1
Urticaria | 8 | 1
Respiratory System | 38 | 4
Increased Cough | 13 | 1
Rhinitis | 12 | 1
Bronchospasm | 8 | 1
Dyspnea | 7 | 1
Sinusitis | 6 | 0
Metabolic and Nutritional Disorders | 38 | 3
Angioedema | 11 | 1
Hyperglycemia | 9 | 1
Peripheral Edema | 8 | 0
LDH Increase | 7 | 0
Digestive System | 37 | 2
Nausea | 23 | 1
Diarrhea | 10 | 1
Vomiting | 10 | 1
Nervous System | 32 | 1
Dizziness | 10 | 1
Anxiety | 5 | 1
Musculoskeletal System | 26 | 3
Myalgia | 10 | 1
Arthralgia | 10 | 1
Cardiovascular System | 25 | 3
Hypotension | 10 | 1
Hypertension | 6 | 1

In these single- arm rituximab studies, bronchiolitis obliterans occurred during and up to 6 months after rituximab infusion.

Previously Untreated, Low-Grade or Follicular, NHL

In NHL Study 4, patients in the R-CVP arm experienced a higher incidence of infusional toxicity and neutropenia compared to patients in the CVP arm. The following adverse reactions occurred more frequently (greater than or equal to 5%) in patients receiving R-CVP compared to CVP alone: rash (17% vs. 5%), cough (15% vs. 6%), flushing (14% vs. 3%), rigors (10% vs. 2%), pruritus (10% vs. 1%), neutropenia (8% vs. 3%), and chest tightness (7% vs. 1%) [see Clinical Studies (14.2)].

In NHL Study 5, detailed safety data collection was limited to serious adverse reactions, Grade greater than or equal to 2 infections, and Grade greater than or equal to 3 adverse reactions. In patients receiving rituximab as single-agent maintenance therapy following rituximab plus chemotherapy, infections were reported more frequently compared to the observation arm (37% vs. 22%). Grade 3-4 adverse reactions occurring at a higher incidence (greater than or equal to 2%) in the rituximab group were infections (4% vs. 1%) and neutropenia (4% vs. less than 1%).

In NHL Study 6, the following adverse reactions were reported more frequently (greater than or equal to 5%) in patients receiving rituximab following CVP compared to patients who received no further therapy: fatigue (39% vs. 14%), anemia (35% vs. 20%), peripheral sensory neuropathy (30% vs. 18%), infections (19% vs. 9%), pulmonary toxicity (18% vs. 10%), hepato-biliary toxicity (17% vs. 7%), rash and/or pruritus (17% vs. 5%), arthralgia (12% vs. 3%), and weight gain (11% vs. 4%). Neutropenia was the only Grade 3 or 4 adverse reaction that occurred more frequently (greater than or equal to 2%) in the rituximab arm compared with those who received no further therapy (4% vs. 1%) [see Clinical Studies (14.3)].

DLBCL

In NHL Studies 7 (NCT00003150) and 8 [see Clinical Studies (14.3)], the following adverse reactions, regardless of severity, were reported more frequently (greater than or equal to 5%) in patients age greater than or equal to 60 years receiving R-CHOP as compared to CHOP alone: pyrexia (56% vs. 46%), lung disorder (31% vs. 24%), cardiac disorder (29% vs. 21%), and chills (13% vs. 4%). Detailed safety data collection in these studies was primarily limited to Grade 3 and 4 adverse reactions and serious adverse reactions.

In NHL Study 8, a review of cardiac toxicity determined that supraventricular arrhythmias or tachycardia accounted for most of the difference in cardiac disorders (4.5% for R-CHOP vs. 1.0% for CHOP).

The following Grade 3 or 4 adverse reactions occurred more frequently among patients in the R-CHOP arm compared with those in the CHOP arm: thrombocytopenia (9% vs. 7%) and lung disorder (6% vs. 3%). Other Grade 3 or 4 adverse reactions occurring more frequently among patients receiving R-CHOP were viral infection (NHL Study 8), neutropenia (NHL Studies 8 and 9 (NCT00064116)), and anemia (NHL Study 9).

CLL

The data below reflect exposure to rituximab in combination with fludarabine and cyclophosphamide in 676 patients with CLL in CLL Study 1 (NCT00281918) or CLL Study 2 (NCT00090051) [see Clinical Studies (14.5)]. The age range was 30–83 years and 71% were men. Detailed safety data collection in CLL Study 1 was limited to Grade 3 and 4 adverse reactions and serious adverse reactions.

Infusion-related adverse reactions were defined by any of the following adverse events occurring during or within 24 hours of the start of infusion: nausea, pyrexia, chills, hypotension, vomiting, and dyspnea.

In CLL Study 1, the following Grade 3 and 4 adverse reactions occurred more frequently in R-FC-treated patients compared to FC-treated patients: infusion-related reactions (9% in R-FC arm), neutropenia (30% vs. 19%), febrile neutropenia (9% vs. 6%), leukopenia (23% vs. 12%), and pancytopenia (3% vs. 1%).

In CLL Study 2, the following Grade 3 or 4 adverse reactions occurred more frequently in R-FC-treated patients compared to FC-treated patients: infusion-related reactions (7% in R-FC arm), neutropenia (49% vs. 44%), febrile neutropenia (15% vs. 12%), thrombocytopenia (11% vs. 9%), hypotension (2% vs. 0%), and hepatitis B (2% vs. < 1%). Fifty-nine percent of R-FC-treated patients experienced an infusion-related reaction of any severity.

Rheumatoid Arthritis

The data presented below reflect the experience in 2,578 RA patients treated with rituximab in controlled and long-term studies [Pooled studies: NCT00074438, NCT00422383, NCT00468546, NCT00299130, NCT00282308, NCT00266227, NCT02693210, NCT02093026 and NCT02097745.] with a total exposure of 5,014 patient-years.

Among all exposed patients, adverse reactions reported in greater than 10% of patients include infusion-related reactions, upper respiratory tract infection, nasopharyngitis, urinary tract infection, and bronchitis.

In placebo-controlled studies, patients received 2 × 500 mg or 2 × 1,000 mg intravenous infusions of rituximab or placebo, in combination with methotrexate, during a 24-week period. From these studies, 938 patients treated with rituximab (2 × 1,000 mg) or placebo have been pooled (see Table 3). Adverse reactions reported in greater than or equal to 5% of patients were hypertension, nausea, upper respiratory tract infection, arthralgia, pyrexia and pruritus (see Table 3). The rates and types of adverse reactions in patients who received rituximab 2 × 500 mg were similar to those observed in patients who received rituximab 2 × 1,000 mg.

Table 3 [These data are based on 938 patients treated in Phase 2 and 3 studies of rituximab (2 × 1,000 mg) or placebo administered in combination with methotrexate.] . Incidence of All Adverse Reactions [Coded using MedDRA.] Occurring in Greater Than or Equal to 2% and at Least 1% Greater than Placebo Among Rheumatoid Arthritis Patients in Clinical Studies Up to Week 24 (Pooled)
Adverse Reactions | Placebo + MTX N=398 n (%) | Rituximab + MTX N=540 n (%)
Hypertension | 21 (5) | 43 (8)
Nausea | 19 (5) | 41 (8)
Upper Respiratory Tract Infection | 23 (6) | 37 (7)
Arthralgia | 14 (4) | 31 (6)
Pyrexia | 8 (2) | 27 (5)
Pruritus | 5 (1) | 26 (5)
Chills | 9 (2) | 16 (3)
Dyspepsia | 3 (< 1) | 16 (3)
Rhinitis | 6 (2) | 14 (3)
Paresthesia | 3 (< 1) | 12 (2)
Urticaria | 3 (< 1) | 12 (2)
Abdominal Pain Upper | 4 (1) | 11 (2)
Throat Irritation | 0 (0) | 11 (2)
Anxiety | 5 (1) | 9 (2)
Migraine | 2 (< 1) | 9 (2)
Asthenia | 1 (< 1) | 9 (2)

Infusion-Related Reactions

In the rituximab RA pooled placebo-controlled studies, 32% of rituximab-treated patients experienced an adverse reaction during or within 24 hours following their first infusion, compared to 23% of placebo-treated patients receiving their first infusion. The incidence of adverse reactions during the 24-hour period following the second infusion, rituximab or placebo, decreased to 11% and 13%, respectively. Acute infusion-related reactions (manifested by fever, chills, rigors, pruritus, urticaria/rash, angioedema, sneezing, throat irritation, cough, and/or bronchospasm, with or without associated hypotension or hypertension) were experienced by 27% of rituximab-treated patients following their first infusion, compared to 19% of placebo-treated patients receiving their first placebo infusion. The incidence of these acute infusion-related reactions following the second infusion of rituximab or placebo decreased to 9% and 11%, respectively. Serious acute infusion-related reactions were experienced by less than 1% of patients in either treatment group. Acute infusion-related reactions required dose modification (stopping, slowing, or interruption of the infusion) in 10% and 2% of patients receiving rituximab or placebo, respectively, after the first course. The proportion of patients experiencing acute infusion-related reactions decreased with subsequent courses of rituximab. The administration of intravenous glucocorticoids prior to rituximab infusions reduced the incidence and severity of such reactions, however, there was no clear benefit from the administration of oral glucocorticoids for the prevention of acute infusion-related reactions. Patients in clinical studies also received antihistamines and acetaminophen prior to rituximab infusions.

Infections

In the pooled, placebo-controlled studies, 39% of patients in the rituximab group experienced an infection of any type compared to 34% of patients in the placebo group. The most common infections were nasopharyngitis, upper respiratory tract infections, urinary tract infections, bronchitis, and sinusitis.

The incidence of serious infections was 2% in the rituximab-treated patients and 1% in the placebo group.

In the experience with rituximab in 2,578 RA patients, the rate of serious infections was 4.31 per 100 patient years. The most common serious infections (greater than or equal to 0.5%) were pneumonia or lower respiratory tract infections, cellulitis and urinary tract infections. Fatal serious infections included pneumonia, sepsis and colitis. Rates of serious infection remained stable in patients receiving subsequent courses. In 185 rituximab-treated RA patients with active disease, subsequent treatment with a biologic DMARD, the majority of which were TNF antagonists, did not appear to increase the rate of serious infection. Thirteen serious infections were observed in 186.1 patient years (6.99 per 100 patient years) prior to exposure and 10 were observed in 182.3 patient years (5.49 per 100 patient years) after exposure.

Cardiovascular Adverse Reactions

In the pooled, placebo-controlled studies, the proportion of patients with serious cardiovascular reactions was 1.7% and 1.3% in the rituximab and placebo treatment groups, respectively. Three cardiovascular deaths occurred during the double-blind period of the RA studies including all rituximab regimens (3/769 = 0.4%) as compared to none in the placebo treatment group (0/389).

In the experience with rituximab in 2,578 RA patients, the rate of serious cardiac reactions was 1.93 per 100 patient years. The rate of myocardial infarction (MI) was 0.56 per 100 patient years (28 events in 26 patients), which is consistent with MI rates in the general RA population. These rates did not increase over three courses of rituximab.

Since patients with RA are at increased risk for cardiovascular events compared with the general population, patients with RA should be monitored throughout the infusion and RIABNI should be discontinued in the event of a serious or life-threatening cardiac event.

Hypophosphatemia and Hyperuricemia

In the pooled, placebo-controlled studies, newly-occurring hypophosphatemia (less than 2.0 mg/dL) was observed in 12% (67/540) of patients on rituximab versus 10% (39/398) of patients on placebo. Hypophosphatemia was more common in patients who received corticosteroids. Newly-occurring hyperuricemia (greater than 10 mg/dL) was observed in 1.5% (8/540) of patients on rituximab versus 0.3% (1/398) of patients on placebo.

In the experience with rituximab in RA patients, newly-occurring hypophosphatemia was observed in 21% (528/2570) of patients and newly-occurring hyperuricemia was observed in 2% (56/2570) of patients. The majority of the observed hypophosphatemia occurred at the time of the infusions and was transient.

Retreatment in Patients with RA

In the experience with rituximab in RA patients, 2,578 patients have been exposed to rituximab and have received up to 10 courses of rituximab in RA clinical trials, with 1,890, 1,043, and 425 patients having received at least two, three, and four courses, respectively. Most of the patients who received additional courses did so 24 weeks or more after the previous course and none were retreated sooner than 16 weeks. The rates and types of adverse reactions reported for subsequent courses of rituximab were similar to rates and types seen for a single course of rituximab.

In RA Study 2, where all patients initially received rituximab, the safety profile of patients who were retreated with rituximab was similar to those who were retreated with placebo [see Clinical Studies (14.6), and Dosage and Administration (2.5)].

Granulomatosis with Polyangiitis (GPA) (Wegener's Granulomatosis) and Microscopic Polyangiitis (MPA)

Induction Treatment of Adult Patients with Active GPA/MPA (GPA/MPA Study 1)

The data presented below from GPA/MPA Study 1 (NCT00104299) reflect the experience in 197 adult patients with active GPA and MPA treated with rituximab or cyclophosphamide in a single controlled study, which was conducted in two phases: a 6-month randomized, double-blind, double-dummy, active-controlled remission induction phase and an additional 12-month remission maintenance phase [see Clinical Studies (14.7)]. In the 6-month remission induction phase, 197 patients with GPA and MPA were randomized to either rituximab 375 mg/m^2 once weekly for 4 weeks plus glucocorticoids, or oral cyclophosphamide 2 mg/kg daily (adjusted for renal function, white blood cell count, and other factors) plus glucocorticoids to induce remission. Once remission was achieved or at the end of the 6-month remission induction period, the cyclophosphamide group received azathioprine to maintain remission. The rituximab group did not receive additional therapy to maintain remission. The primary analysis was at the end of the 6-month remission induction period and the safety results for this period are described below.

Adverse reactions presented below in Table 4 were adverse events which occurred at a rate of greater than or equal to 10% in the rituximab group. This table reflects experience in 99 GPA and MPA patients treated with rituximab, with a total of 47.6 patient-years of observation and 98 GPA and MPA patients treated with cyclophosphamide, with a total of 47.0 patient-years of observation. Infection was the most common category of adverse events reported (47-62%) and is discussed below.

Table 4. Incidence of All Adverse Reactions Occurring in Greater Than or Equal to 10% of Rituximab-treated Patients with Active GPA and MPA in the GPA/MPA Study 1 Up to Month 6 [The study design allowed for crossover or treatment by best medical judgment, and 13 patients in each treatment group received a second therapy during the 6 month study period.]
Adverse Reaction | Rituximab N = 99 n (%) | Cyclophosphamide N = 98 n (%)
Nausea | 18 (18%) | 20 (20%)
Diarrhea | 17 (17%) | 12 (12%)
Headache | 17 (17%) | 19 (19%)
Muscle spasms | 17 (17%) | 15 (15%)
Anemia | 16 (16%) | 20 (20%)
Peripheral edema | 16 (16%) | 6 (6%)
Insomnia | 14 (14%) | 12 (12%)
Arthralgia | 13 (13%) | 9 (9%)
Cough | 13 (13%) | 11 (11%)
Fatigue | 13 (13%) | 21 (21%)
Increased ALT | 13 (13%) | 15 (15%)
Hypertension | 12 (12%) | 5 (5%)
Epistaxis | 11 (11%) | 6 (6%)
Dyspnea | 10 (10%) | 11 (11%)
Leukopenia | 10 (10%) | 26 (27%)
Rash | 10 (10%) | 17 (17%)

Infusion-Related Reactions

Infusion-related reactions in GPA/MPA Study 1 were defined as any adverse event occurring within 24 hours of an infusion and considered to be infusion-related by investigators. Among the 99 patients treated with rituximab, 12% experienced at least one infusion-related reaction, compared with 11% of the 98 patients in the cyclophosphamide group. Infusion-related reactions included cytokine release syndrome, flushing, throat irritation, and tremor. In the rituximab group, the proportion of patients experiencing an infusion-related reaction was 12%, 5%, 4%, and 1% following the first, second, third, and fourth infusions, respectively. Patients were pre-medicated with antihistamine and acetaminophen before each rituximab infusion and were on background oral corticosteroids which may have mitigated or masked an infusion-related reaction; however, there is insufficient evidence to determine whether premedication diminishes the frequency or severity of infusion-related reactions.

Infections

In GPA/MPA Study 1, 62% (61/99) of patients in the rituximab group experienced an infection of any type compared to 47% (46/98) patients in the cyclophosphamide group by Month 6. The most common infections in the rituximab group were upper respiratory tract infections, urinary tract infections, and herpes zoster.

The incidence of serious infections was 11% in the rituximab-treated patients and 10% in the cyclophosphamide treated patients, with rates of approximately 25 and 28 per 100 patient-years, respectively. The most common serious infection was pneumonia.

Hypogammaglobulinemia

Hypogammaglobulinemia (IgA, IgG or IgM below the lower limit of normal) has been observed in patients with GPA and MPA treated with rituximab in GPA/MPA Study 1. At 6 months, in the rituximab group, 27%, 58% and 51% of patients with normal immunoglobulin levels at baseline, had low IgA, IgG and IgM levels, respectively compared to 25%, 50% and 46% in the cyclophosphamide group.

Follow up Treatment of Adult Patients with GPA/MPA who have Achieved Disease Control with Induction Treatment (GPA/MPA Study 2)

In GPA/MPA Study 2 (NCT00748644), an open-label, controlled, clinical study [see Clinical Studies (14.7)], evaluating the efficacy and safety of non-U.S.-licensed rituximab versus azathioprine as follow up treatment in adult patients with GPA, MPA or renal-limited ANCA-associated vasculitis who had achieved disease control after induction treatment with cyclophosphamide, a total of 57 GPA and MPA patients in disease remission received follow up treatment with two 500 mg intravenous infusions of non-U.S.-licensed rituximab, separated by two weeks on Day 1 and Day 15, followed by a 500 mg intravenous infusion every 6 months for 18 months.

The safety profile was consistent with the safety profile for rituximab in RA, GPA and MPA.

Infusion-Related Reactions

In GPA/MPA Study 2, 7/57 (12%) patients in the non-U.S.-licensed rituximab arm reported infusion-related reactions. The incidence of IRR symptoms was highest during or after the first infusion (9%) and decreased with subsequent infusions (less than 4%). One patient had two serious IRRs, two IRRs led to a dose modification, and no IRRs were severe, fatal, or led to withdrawal from the study.

Infections

In GPA/MPA Study 2, 30/57 (53%) patients in the non-U.S.-licensed rituximab arm and 33/58 (57%) in the azathioprine arm reported infections. The incidence of all grade infections was similar between the arms. The incidence of serious infections was similar in both arms (12%). The most commonly reported serious infection in the group was mild or moderate bronchitis.

Long-term, Observational Study with Rituximab in Patients with GPA/MPA (GPA/MPA Study 3)

In a long-term observational safety study (NCT01613599), 97 patients with GPA or MPA received treatment with rituximab (mean of 8 infusions [range 1-28]) for up to 4 years, according to physician standard practice and discretion. Majority of patients received doses ranging from 500 mg to 1,000 mg, approximately every 6 months. The safety profile was consistent with the safety profile for rituximab in RA, GPA and MPA.

Pemphigus Vulgaris (PV)

PV Study 1

PV Study 1 (NCT00784589), a randomized, controlled, multicenter open-label study, evaluated the efficacy and safety of non-U.S.-licensed rituximab in combination with short-term prednisone compared to prednisone monotherapy in 90 patients (74 Pemphigus Vulgaris [PV] patients and 16 Pemphigus Foliaceus [PF] patients) [see Clinical Studies (14.8)]. Safety results for the PV patient population during the 24-month treatment period are described below.

The safety profile of the non-U.S.-licensed rituximab in patients with PV was consistent with that observed in patients with rituximab-treated RA and GPA and MPA [see Adverse Reactions (6.1)].

Adverse reactions from PV Study 1 are presented below in Table 5 and were adverse events which occurred at a rate greater than or equal to 5% among PV patients treated with non-U.S.-licensed rituximab and with at least 2% absolute difference in incidence between the group treated with non-U.S.-licensed rituximab and the prednisone monotherapy group up to Month 24. No patients in the group treated with non-U.S.-licensed rituximab withdrew due to adverse reactions. The clinical study did not include sufficient number of patients to allow for direct comparison of adverse reaction rates between treatment groups.

Table 5. Incidence of All Adverse Reactions Occurring in greater than or equal to 5% Among PV Patients Treated with Non-U.S.-licensed Rituximab and with at Least 2% Absolute Difference in Incidence Between the Group Treated with Non-U.S.-licensed Rituximab with Short-term Prednisone and the Group Treated with Prednisone Monotherapy in PV Study 1 (Up to Month 24)
Adverse Reactions | Non-U.S.-licensed Rituximab + Short-term Prednisone N = 38 n (%) | Prednisone N = 36 n (%)
Infusion-related reactions [Infusion-related reactions included symptoms collected on the next scheduled visit after each infusion, and adverse reactions occurring on the day of or one day after the infusion. The most common infusion-related reactions included headaches, chills, high blood pressure, nausea, asthenia, and pain.] | 22 (58%) | N/A
Depression | 7 (18%) | 4 (11%)
Herpes simplex | 5 (13%) | 1 (3%)
Alopecia | 5 (13%) | 0 (0%)
Fatigue | 3 (8%) | 2 (6%)
Abdominal pain upper | 2 (5%) | 1 (3%)
Conjunctivitis | 2 (5%) | 0 (0%)
Dizziness | 2 (5%) | 0 (0%)
Headache | 2 (5%) | 1 (3%)
Herpes zoster | 2 (5%) | 1 (3%)
Irritability | 2 (5%) | 0 (0%)
Musculoskeletal pain | 2 (5%) | 0 (0%)
Pruritus | 2 (5%) | 0 (0%)
Pyrexia | 2 (5%) | 0 (0%)
Skin disorder | 2 (5%) | 0 (0%)
Skin papilloma | 2 (5%) | 0 (0%)
Tachycardia | 2 (5%) | 0 (0%)
Urticaria | 2 (5%) | 0 (0%)
N/A = not applicable

Infusion-Related Reactions

Infusion-related reactions were the most commonly reported adverse drug reactions (58%, 22 patients). All infusion-related reactions were mild to moderate (Grade 1 or 2) except one Grade 3 serious infusion-related reaction (arthralgia) associated with the Month 12 maintenance infusion. The proportion of patients experiencing an infusion-related reaction was 29% (11 patients), 40% (15 patients), 13% (5 patients), and 10% (4 patients) following the first, second, third, and fourth infusions, respectively. No patients were withdrawn from treatment due to infusion-related reactions. Symptoms of infusion-related reactions were similar in type and severity to those seen in RA and GPA and MPA patients [see Adverse Reactions (6.1)].

Infections

Fourteen patients (37%) in the group treated with non-U.S.-licensed rituximab experienced treatment-related infections compared to 15 patients (42%) in the prednisone group. The most common infections in the group treated with non-U.S.-licensed rituximab were herpes simplex, herpes zoster, bronchitis, urinary tract infection, fungal infection, and conjunctivitis. Three patients (8%) in the group treated with non-U.S.-licensed rituximab experienced a total of 5 serious infections (Pneumocystis jirovecii pneumonia, infective thrombosis, intervertebral discitis, lung infection, Staphylococcal sepsis) and 1 patient (3%) in the prednisone group experienced 1 serious infection (Pneumocystis jirovecii pneumonia).

PV Study 2

In PV Study 2 (NCT02383589), a randomized, double-blind, double-dummy, active-comparator, multicenter study evaluating the efficacy and safety of rituximab compared to mycophenolate mofetil (MMF) in patients with moderate-to-severe PV requiring oral corticosteroids, 67 PV patients received treatment with rituximab (initial 1,000 mg IV on Study Day 1 and a second 1,000 mg IV on Study Day 15 repeated at Weeks 24 and 26) for up to 52 weeks [see Clinical Studies (14.8)].

In PV Study 2, ADR defined as adverse events occurring in greater than or equal to 5% of patients in the rituximab arms and assessed as related are shown in Table 6.

Table 6. Incidence of All Adverse Reactions occurring in greater than or equal to 5% of Rituximab-treated Pemphigus Vulgaris Patients (N = 67) from PV Study 2 (up to Week 52)
Adverse Reactions | Rituximab (N = 67)
Infusion-related reactions | 15 (22%) [The most common infusion-related reaction symptoms/Preferred Terms for PV Study 2 in the rituximab arm were dyspnea, erythema, hyperhidrosis, flushing/hot flush, hypotension/low blood pressure and rash/rash pruritic]
Upper respiratory tract infection/ Nasopharyngitis | 11 (16%)
Headache | 10 (15%)
Asthenia/Fatigue | 9 (13%)
Oral candidiasis | 6 (9%)
Arthralgia | 6 (9%)
Back pain | 6 (9%)
Urinary tract infection | 5 (8%)
Dizziness | 4 (6%)

Infusion-Related Reactions

In PV Study 2, IRRs occurred primarily at the first infusion and the frequency of IRRs decreased with subsequent infusions: 17.9%, 4.7%, 3.5% and 3.5% of patients experienced IRRs at the first, second, third, and fourth infusions, respectively. In 11/15 patients who experienced at least one IRR, the IRRs were Grade 1 or 2. In 4/15 patients, Grade greater than or equal to 3 IRRs were reported and led to discontinuation of rituximab treatment; three of the four patients experienced serious [life-threatening] IRRs. Serious IRRs occurred at the first (2 patients) or second (1 patient) infusion and resolved with symptomatic treatment.

Infections

In PV Study 2, 42/67 patients (62.7%) in the rituximab arm experienced infections. The most common infections in the rituximab arm were upper respiratory tract infection, nasopharyngitis, oral candidiasis and urinary tract infection. Six patients (9%) in the rituximab arm experienced serious infections.

Laboratory Abnormalities

In PV Study 2, in the rituximab arm, transient decreases in T-cell lymphocytes and phosphorus level were very commonly observed post-infusion. In some cases, treatment of hypophosphatemia was required.

Hypogammaglobulinemia (IgG or IgM below the lower limit of normal), including prolonged hypogammaglobulinemia (defined as Ig levels below lower limit of normal for at least 4 months) was observed in PV Study 2. Based on levels less than LLN measured at Week 16, Week 24, Week 40, and Week 52, 16.4% (11/67) of patients with normal baseline immunoglobulins had prolonged hypogammaglobulinemia (10 patients – IgM, 1 patient – both IgG and IgM) after treatment with rituximab.

6.2 Immunogenicity

The observed incidence of anti-drug antibodies is highly dependent on the sensitivity and specificity of the assay. Differences in assay methods preclude meaningful comparisons of the incidence of anti-drug antibodies in the studies described below with the incidence of anti-drug antibodies in other studies, including those of rituximab or of other rituximab products.

Using an ELISA assay, anti-rituximab antibody was detected in 4 of 356 (1.1%) patients with low-grade or follicular NHL receiving single-agent rituximab. Three of the four patients had an objective clinical response.

A total of 273/2578 (11%) patients with RA tested positive for anti-rituximab antibodies at any time after receiving rituximab. Anti-rituximab antibody positivity was not associated with increased rates of infusion-related reactions or other adverse events. Upon further treatment, the proportions of patients with infusion-related reactions were similar between anti-rituximab antibody positive and negative patients, and most reactions were mild to moderate. Four anti-rituximab antibody positive patients had serious infusion-related reactions, and the temporal relationship between anti-rituximab antibody positivity and infusion-related reaction was variable.

A total of 23/99 (23%) rituximab-treated adult patients with GPA and MPA developed anti-rituximab antibodies by 18 months in GPA/MPA Study 1. The clinical relevance of anti-rituximab antibody formation in rituximab-treated adult patients is unclear.

Using a new ELISA assay, a total of 19/34 (56%) patients with PV, who were treated with non-U.S.-licensed rituximab, tested positive for anti-rituximab antibodies by 18 months in PV Study 1. In PV Study 2, a total of 20/63 (32%) rituximab-treated PV patients tested positive for ADA by week 52 (19 patients had treatment-inducted ADA and 1 patient had treatment-enhanced ADA). The clinical relevance of anti-rituximab antibody formation in rituximab-treated PV patients is unclear.

6.3 Postmarketing Experience

The following adverse reactions have been identified during post-approval use of rituximab. Because these reactions are reported voluntarily from a population of uncertain size, it is not always possible to reliably estimate their frequency or establish a causal relationship to drug exposure.

- Hematologic: prolonged pancytopenia, marrow hypoplasia, Grade 3-4 prolonged or late-onset neutropenia, hyperviscosity syndrome in Waldenstrom's macroglobulinemia, prolonged hypogammaglobulinemia [see Warnings and Precautions (5.6)].
- Cardiac: fatal cardiac failure.
- Immune/Autoimmune Events: uveitis, optic neuritis, systemic vasculitis, pleuritis, lupus-like syndrome, serum sickness, polyarticular arthritis, and vasculitis with rash.
- Infection: viral infections, including progressive multifocal leukoencephalopathy (PML), increase in fatal infections in HIV-associated lymphoma, and a reported increased incidence of Grade 3 and 4 infections [see Warnings and Precautions (5.6)].
- Neoplasia: disease progression of Kaposi's sarcoma.
- Skin: severe mucocutaneous reactions, pyoderma gangrenosum (including genital presentation).
- Gastrointestinal: bowel obstruction and perforation.
- Pulmonary: fatal bronchiolitis obliterans and fatal interstitial lung disease.
- Nervous system: Posterior Reversible Encephalopathy Syndrome (PRES)/Reversible Posterior Leukoencephalopathy Syndrome (RPLS).

7 DRUG INTERACTIONS

Formal drug interaction studies have not been performed with rituximab products. In patients with CLL, rituximab did not alter systemic exposure to fludarabine or cyclophosphamide. In clinical trials of patients with RA, concomitant administration of methotrexate or cyclophosphamide did not alter the pharmacokinetics of rituximab.

8 USE IN SPECIFIC POPULATIONS

8.1 Pregnancy

Risk Summary

Based on human data, rituximab products can cause adverse developmental outcomes including B-cell lymphocytopenia in infants exposed in utero (see Clinical Considerations). In animal reproduction studies, intravenous administration of rituximab to pregnant cynomolgus monkeys during the period of organogenesis caused lymphoid B-cell depletion in the newborn offspring at doses resulting in 80% of the exposure (based on AUC) of those achieved following a dose of 2 grams in humans. Advise pregnant women of the risk to a fetus.

Adverse outcomes in pregnancy occur regardless of the health of the mother or the use of medications. The background risk of major birth defects and miscarriage for the indicated populations is unknown. The estimated background risk in the U.S. general population of major birth defects is 2%-4% and of miscarriage is 15%-20% of clinically recognized pregnancies.

Clinical Considerations

Fetal/Neonatal Adverse Reactions

Observe newborns and infants for signs of infection and manage accordingly.

Data

Human Data

Postmarketing data indicate that B-cell lymphocytopenia generally lasting less than 6 months can occur in infants exposed to rituximab in utero. Rituximab was detected postnatally in the serum of infants exposed in utero.

Animal Data

An embryo-fetal developmental toxicity study was performed on pregnant cynomolgus monkeys. Pregnant animals received rituximab via the intravenous route during early gestation (organogenesis period; post coitum Days 20 through 50). Rituximab was administered as loading doses on post coitum (PC) Days 20, 21 and 22, at 15, 37.5 or 75 mg/kg/day, and then weekly on PC Days 29, 36, 43 and 50, at 20, 50 or 100 mg/kg/week. The 100 mg/kg/week dose resulted in 80% of the exposure (based on AUC) of those achieved following a dose of 2 grams in humans. Rituximab crosses the monkey placenta. Exposed offspring did not exhibit any teratogenic effects but did have decreased lymphoid tissue B cells.

A subsequent pre-and postnatal reproductive toxicity study in cynomolgus monkeys was completed to assess developmental effects including the recovery of B cells and immune function in infants exposed to rituximab in utero. Animals were treated with a loading dose of 0, 15, or 75 mg/kg every day for 3 days, followed by weekly dosing with 0, 20, or 100 mg/kg dose. Subsets of pregnant females were treated from PC Day 20 through postpartum Day 78, PC Day 76 through PC Day 134, and from PC Day 132 through delivery and postpartum Day 28. Regardless of the timing of treatment, decreased B cells and immunosuppression were noted in the offspring of rituximab-treated pregnant animals. The B-cell counts returned to normal levels, and immunologic function was restored within 6 months postpartum.

8.2 Lactation

There are limited data on the presence of rituximab in human milk and the effect on the breastfed child, and there are no data on the effect on milk production. Rituximab is detected in the milk of lactating cynomolgus monkeys, and maternal IgG is present in human breast milk. Rituximab has also been reported to be excreted at low concentrations in human breast milk. Given that the clinical significance of this finding for children is not known, advise women not to breastfeed during treatment with RIABNI and for 6 months after the last dose due to the potential of serious adverse reactions in breastfed children.

8.3 Females and Males of Reproductive Potential

Rituximab products can cause fetal harm when administered to a pregnant woman [see Use in Specific Populations (8.1)].

Pregnancy Testing

Verify pregnancy status in females of reproductive potential prior to initiating RIABNI.

Contraception

Females

Advise females of reproductive potential to use effective contraception during treatment with RIABNI and for 12 months after the last dose.

8.4 Pediatric Use

A pediatric assessment for RIABNI demonstrates that RIABNI is safe and effective for pediatric patients in an indication for which Rituxan (rituximab) is approved. However, RIABNI is not approved for such indication due to marketing exclusivity for Rituxan (rituximab). The safety and effectiveness of RIABNI have not been established in pediatric patients less than 2 years of age for GPA and MPA.

The safety and effectiveness of RIABNI have not been established in pediatric patients with CLL.

Rheumatoid Arthritis and Pemphigus Vulgaris

The safety and effectiveness of RIABNI have not been established in pediatric patients with PV or RA.

Rituximab was not studied in pediatric patients with polyarticular juvenile idiopathic arthritis (PJIA) due to concerns regarding the potential for prolonged immunosuppression as a result of B-cell depletion in the developing juvenile immune system.

8.5 Geriatric Use

Diffuse Large B-Cell NHL

Among patients with DLBCL evaluated in three randomized, active-controlled trials, 927 patients received rituximab in combination with chemotherapy. Of these, 396 (43%) were age 65 or greater and 123 (13%) were age 75 or greater. No overall differences in effectiveness were observed between these patients and younger patients. Cardiac adverse reactions, mostly supraventricular arrhythmias, occurred more frequently among elderly patients. Serious pulmonary adverse reactions were also more common among the elderly, including pneumonia and pneumonitis.

Low-Grade or Follicular Non-Hodgkin's Lymphoma

Patients with previously untreated follicular NHL evaluated in NHL Study 5 were randomized to rituximab as single-agent maintenance therapy (n = 505) or observation (n = 513) after achieving a response to rituximab in combination with chemotherapy. Of these, 123 (24%) patients in the rituximab arm were age 65 or older. No overall differences in safety or effectiveness were observed between these patients and younger patients. Other clinical studies of rituximab in low-grade or follicular, CD20-positive, B-cell NHL did not include sufficient numbers of patients aged 65 and over to determine whether they respond differently from younger subjects.

Chronic Lymphocytic Leukemia

Among patients with CLL evaluated in two randomized active-controlled trials, 243 of 676 rituximab-treated patients (36%) were 65 years of age or older; of these, 100 rituximab-treated patients (15%) were 70 years of age or older.

In exploratory analyses defined by age, there was no observed benefit from the addition of rituximab to fludarabine and cyclophosphamide among patients 70 years of age or older in CLL Study 1 or in CLL Study 2; there was also no observed benefit from the addition of rituximab to fludarabine and cyclophosphamide among patients 65 years of age or older in CLL Study 2 [see Clinical Studies (14.5)]. Patients 70 years or older received lower dose intensity of fludarabine and cyclophosphamide compared to younger patients, regardless of the addition of rituximab. In CLL Study 1, the dose intensity of rituximab was similar in older and younger patients, however in CLL Study 2 older patients received a lower dose intensity of rituximab.

The incidence of Grade 3 and 4 adverse reactions was higher among patients receiving R-FC who were 70 years or older compared to younger patients for neutropenia [44% vs. 31% (CLL Study 1); 56% vs. 39% (CLL Study 2)], febrile neutropenia [16% vs. 6% (NHL Study 10 (NCT00719472)], anemia [5% vs. 2% (CLL Study 1); 21% vs. 10% (CLL Study 2)], thrombocytopenia [19% vs. 8% (CLL Study 2)], pancytopenia [7% vs. 2% (CLL Study 1); 7% vs. 2% (CLL Study 2)] and infections [30% vs. 14% (CLL Study 2)].

Rheumatoid Arthritis

Among the 2,578 patients in global RA studies completed to date, 12% were 65–75 years old and 2% were 75 years old and older. The incidences of adverse reactions were similar between older and younger patients. The rates of serious adverse reactions, including serious infections, malignancies, and cardiovascular events were higher in older patients.

Granulomatosis with Polyangiitis (GPA) (Wegener's Granulomatosis) and Microscopic Polyangiitis

Of the 99 rituximab-treated GPA and MPA patients in GPA/MPA Study 1, 36 (36%) were 65 years old and over, while 8 (8%) were 75 years and over. No overall differences in efficacy were observed between patients that were 65 years old and over and younger patients. The overall incidence and rate of all serious adverse events was higher in patients 65 years old and over. The clinical study did not include sufficient numbers of patients aged 65 and over to determine whether they respond differently from younger subjects.

In GPA/MPA Study 2, 30 (26%) of the enrolled patients were at least 65 years old, of which 12 patients were exposed to non-U.S.-licensed rituximab and 18 were exposed to azathioprine. The clinical study did not include sufficient numbers of patients aged 65 and over to determine whether they respond differently from younger subjects.

Pemphigus Vulgaris

Of the 46 patients treated with non-U.S.-licensed rituximab, 15 (33%) patients were 65 years of age and older. The clinical study did not include sufficient numbers of patients aged 65 and older to determine whether they respond differently from younger patients.

11 DESCRIPTION

Rituximab-arrx is a genetically engineered chimeric murine/human monoclonal IgG1 kappa antibody directed against the CD20 antigen. Rituximab-arrx has an approximate molecular weight of 145 kD.

Rituximab-arrx is produced in a mammalian cell (Chinese Hamster Ovary) suspension culture in a nutrient medium.

RIABNI (rituximab-arrx) injection is a sterile, preservative-free, clear to slightly opalescent, colorless to slightly yellow solution for intravenous infusion. RIABNI is supplied at a concentration of 10 mg/mL in either 100 mg/10 mL or 500 mg/50 mL single-dose vials. Each mL of solution contains 10 mg rituximab-arrx, polysorbate 80 (0.7 mg), sodium chloride (9 mg), sodium citrate dihydrate (7.35 mg), and Water for Injection, USP. Hydrochloric acid is used to adjust the buffer solution pH. The pH is 6.5.

12 CLINICAL PHARMACOLOGY

12.1 Mechanism of Action

Rituximab-arrx is a monoclonal antibody. Rituximab products target the CD20 antigen expressed on the surface of pre-B and mature B-lymphocytes. Upon binding to CD20, rituximab products mediate B-cell lysis. Possible mechanisms of cell lysis include complement dependent cytotoxicity (CDC) and antibody dependent cell mediated cytotoxicity (ADCC). B cells are believed to play a role in the pathogenesis of rheumatoid arthritis (RA) and associated chronic synovitis. In this setting, B cells may be acting at multiple sites in the autoimmune/inflammatory process, including through production of rheumatoid factor (RF) and other autoantibodies, antigen presentation, T-cell activation, and/or proinflammatory cytokine production.

12.2 Pharmacodynamics

Non-Hodgkin's Lymphoma (NHL)

In NHL patients, administration of rituximab resulted in depletion of circulating and tissue-based B cells. Among 166 patients in NHL Study 1 (NCT000168740), circulating CD19-positive B cells were depleted within the first three weeks with sustained depletion for up to 6 to 9 months post treatment in 83% of patients. B-cell recovery began at approximately 6 months and median B-cell levels returned to normal by 12 months following completion of treatment.

There were sustained and statistically significant reductions in both IgM and IgG serum levels observed from 5 through 11 months following rituximab administration; 14% of patients had IgM and/or IgG serum levels below the normal range.

Rheumatoid Arthritis

In RA patients, treatment with rituximab induced depletion of peripheral B lymphocytes, with the majority of patients demonstrating near complete depletion (CD19 counts below the lower limit of quantification, 20 cells/µL) within 2 weeks after receiving the first dose of rituximab. The majority of patients showed peripheral B-cell depletion for at least 6 months. A small proportion of patients (~4%) had prolonged peripheral B-cell depletion lasting more than 3 years after a single course of treatment.

Total serum immunoglobulin levels, IgM, IgG, and IgA were reduced at 6 months with the greatest change observed in IgM. At Week 24 of the first course of rituximab treatment, small proportions of patients experienced decreases in IgM (10%), IgG (2.8%), and IgA (0.8%) levels below the lower limit of normal (LLN). In the experience with rituximab in RA patients during repeated rituximab treatment, 23.3%, 5.5%, and 0.5% of patients experienced decreases in IgM, IgG, and IgA concentrations below LLN at any time after receiving rituximab, respectively. The clinical consequences of decreases in immunoglobulin levels in RA patients treated with rituximab are unclear.

Treatment with rituximab in patients with RA was associated with reduction of certain biologic markers of inflammation such as interleukin-6 (IL-6), C-reactive protein (CRP), serum amyloid protein (SAA), S100 A8/S100 A9 heterodimer complex (S100 A8/9), anti-citrullinated peptide (anti-CCP), and RF.

Granulomatosis with Polyangiitis (GPA) (Wegener's Granulomatosis) and Microscopic Polyangiitis

In GPA and MPA patients in GPA/MPA Study 1, peripheral blood CD19 B-cells depleted to less than 10 cells/µL following the first two infusions of rituximab, and remained at that level in most (84%) patients through Month 6. By Month 12, the majority of patients (81%) showed signs of B-cell return with counts greater than 10 cells/µL. By Month 18, most patients (87%) had counts greater than 10 cells/µL.

In GPA/MPA Study 2 where patients received non-U.S.-licensed rituximab as two 500 mg intravenous infusions separated by two weeks, followed by a 500 mg intravenous infusion at Month 6, 12, and 18, 70% (30 out of 43) of the rituximab-treated patients with CD19+ peripheral B cells evaluated post-baseline had undetectable CD19+ peripheral B cells at Month 24. At Month 24, all 37 patients with evaluable baseline CD19+ peripheral B cells and Month 24 measurements had lower CD19+ B cells relative to baseline.

12.3 Pharmacokinetics

Non-Hodgkin's Lymphoma (NHL)

Pharmacokinetics were characterized in 203 NHL patients receiving 375 mg/m^2 rituximab weekly by intravenous infusion for 4 doses. Rituximab was detectable in the serum of patients 3 to 6 months after completion of treatment.

The pharmacokinetic profile of rituximab when administered as 6 infusions of 375 mg/m^2 in combination with 6 cycles of CHOP chemotherapy was similar to that seen with rituximab alone.

Based on a population pharmacokinetic analysis of data from 298 NHL patients who received rituximab once weekly or once every three weeks, the estimated median terminal elimination half-life was 22 days (range, 6.1 to 52 days). Patients with higher CD19-positive cell counts or larger measurable tumor lesions at pretreatment had a higher clearance. However, dose adjustment for pretreatment CD19 count or size of tumor lesion is not necessary. Age and gender had no effect on the pharmacokinetics of rituximab.

Pharmacokinetics were characterized in 21 patients with CLL receiving rituximab according to the recommended dose and schedule. The estimated median terminal half-life of rituximab was 32 days (range, 14 to 62 days).

Rheumatoid Arthritis

Following administration of 2 doses of rituximab in patients with RA, the mean (± S.D.; % CV) concentrations after the first infusion (Cmax first) and second infusion (Cmax second) were 157 (± 46; 29%) and 183 (± 55; 30%) mcg/mL, and 318 (± 86; 27%) and 381 (± 98; 26%) mcg/mL for the 2 × 500 mg and 2 × 1,000 mg doses, respectively.

Based on a population pharmacokinetic analysis of data from 2,005 RA patients who received rituximab, the estimated clearance of rituximab was 0.335 L/day; volume of distribution was 3.1 L and mean terminal elimination half-life was 18.0 days (range, 5.17 to 77.5 days). Age, weight and gender had no effect on the pharmacokinetics of rituximab in RA patients.

Granulomatosis with Polyangiitis (GPA) (Wegener's Granulomatosis) and Microscopic Polyangiitis

The pharmacokinetic parameters in adult patients with GPA/MPA receiving 375 mg/m^2 intravenous rituximab or non-U.S.-licensed rituximab once weekly for four doses are summarized in Table 7.

Table 7. Population PK in Adult Patients with GPA/MPA
Parameter | Statistic | GPA/MPA Study 1
N | Number of Patients | 97
Terminal Half-life (days) | Median (Range) | 25 (11 to 52)
AUC0-180d (µg/mL*day) | Median (Range) | 10,302 (3,653 to 21,874)
Clearance (L/day) | Median (Range) | 0.279 (0.113 to 0.653)
Volume of Distribution (L) | Median (Range) | 3.12 (2.42 to 3.91)

The population PK analysis in adults with GPA and MPA showed that male patients and patients with higher BSA or positive anti-rituximab antibody levels have higher clearance. However, further dose adjustment based on gender or anti-drug antibody status is not necessary.

Pemphigus Vulgaris

The PK parameters in adult PV patients receiving 1,000 mg IV infusion of rituximab at Days 1, 15, 168, and 182 are summarized in Table 8.

Table 8. Population PK in adult PV patients from PV Study 2
Parameter | Infusion Cycle
 | 1st cycle of 1,000 mg Day 1 and Day 15 N = 67 | 2nd cycle of 1,000 mg Day 168 and Day 182 N = 67
Terminal Half-life (days)
Median | 21.1 | 26.2
(Range) | (9.3 to 36.2) | (16.4 to 42.8)
Clearance (L/day)
Median | 0.30 | 0.24
(Range) | (0.16 to 1.51) | (0.13 to 0.45)
Central Volume of Distribution (L)
Median | 3.49 | 3.49
(Range) | (2.48 to 5.22) | (2.48 to 5.22)

Following the first cycle of rituximab administration, the PK parameters of rituximab in patients with PV were similar to those in patients with RA and in patients with GPA/MPA. Following the 2nd cycle of rituximab administration, rituximab clearance decreased by 22% assuming Pemphigus Disease Area Index (PDAI) activity score of 0 at the start of both cycles, while the central volume of distribution remained unchanged. The presence of anti-rituximab antibodies was associated with a higher clearance resulting in lower rituximab concentrations.

Specific Populations

The clearance and volume of distribution of rituximab increased with increasing body surface area (BSA).

No formal studies were conducted to examine the effects of either renal or hepatic impairment on the pharmacokinetics of rituximab products.

Drug Interaction Studies

Formal drug interaction studies have not been performed with rituximab products.

13 NONCLINICAL TOXICOLOGY

13.1 Carcinogenesis, Mutagenesis, Impairment of Fertility

No long-term animal studies have been performed to establish the carcinogenic or mutagenic potential of rituximab products or to determine potential effects on fertility in males or females.

14 CLINICAL STUDIES

14.1 Relapsed or Refractory, Low-Grade or Follicular, CD20-Positive, B-Cell NHL

The safety and effectiveness of rituximab in relapsed, refractory CD20+ NHL were demonstrated in 3 single-arm studies enrolling 296 patients.

NHL Study 1

A multicenter, open-label, single-arm study was conducted in 166 patients with relapsed or refractory, low-grade or follicular, B-cell NHL who received 375 mg/m^2 of rituximab given as an intravenous infusion weekly for 4 doses. Patients with tumor masses > 10 cm or with > 5,000 lymphocytes/µL in the peripheral blood were excluded from the study.

Results are summarized in Table 9. The median time to onset of response was 50 days. Disease-related signs and symptoms (including B-symptoms) resolved in 64% (25/39) of those patients with such symptoms at study entry.

NHL Study 2

In a multicenter, single-arm study, 37 patients with relapsed or refractory, low-grade NHL received 375 mg/m^2 of rituximab weekly for 8 doses. Results are summarized in Table 9.

NHL Study 3

In a multicenter, single-arm study, 60 patients received 375 mg/m^2 of rituximab weekly for 4 doses. All patients had relapsed or refractory, low-grade or follicular, B-cell NHL and had achieved an objective clinical response to rituximab administered 3.8–35.6 months (median 14.5 months) prior to retreatment with rituximab. Of these 60 patients, 5 received more than one additional course of rituximab. Results are summarized in Table 9.

Bulky Disease

In pooled data from studies 1 and 3, 39 patients with bulky (single lesion > 10 cm in diameter) and relapsed or refractory, low-grade NHL received rituximab 375 mg/m^2 weekly for 4 doses. Results are summarized in Table 9.

Table 9. Summary of Rituximab Efficacy Data in NHL by Schedule and Clinical Setting
 | Study 1 Weekly × 4 N = 166 | Study 2 Weekly × 8 N = 37 | Study 1 and Study 3 Bulky disease, Weekly × 4 N = 39 [Six of these patients are included in the first column. Thus, data from 296 intent-to-treat patients are provided in this table.] | Study 3 Retreatment, Weekly × 4 N = 60
Overall Response Rate | 48% | 57% | 36% | 38%
Complete Response Rate | 6% | 14% | 3% | 10%
Median Duration of Response [Kaplan-Meier projected with observed range.] , ["+" indicates an ongoing response.] , [Duration of response: interval from the onset of response to disease progression.] | 11.2 | 13.4 | 6.9 | 15.0
(Months) [Range] | [1.9 to 42.1+] | [2.5 to 36.5+] | [2.8 to 25.0+] | [3.0 to 25.1+]

14.2 Previously Untreated, Low-Grade or Follicular, CD20-Positive, B-Cell NHL

The safety and effectiveness of rituximab in previously untreated, low-grade or follicular, CD20+ NHL were demonstrated in 3 randomized, controlled trials enrolling 1,662 patients.

NHL Study 4

A total of 322 patients with previously untreated follicular NHL were randomized (1:1) to receive up to eight 3-week cycles of CVP chemotherapy alone (CVP) or in combination with rituximab 375 mg/m^2 on Day 1 of each cycle (R-CVP) in an open-label, multicenter study. The main outcome measure of the study was progression-free survival (PFS) defined as the time from randomization to the first of progression, relapse, or death.

Twenty-six percent of the study population was > 60 years of age, 99% had Stage III or IV disease, and 50% had an International Prognostic Index (IPI) score greater than or equal to 2. The results for PFS as determined by a blinded, independent assessment of progression are presented in Table 10. The point estimates may be influenced by the presence of informative censoring. The PFS results based on investigator assessment of progression were similar to those obtained by the independent review assessment.

Table 10. Efficacy Results in NHL Study 4
 | Study Arm
 | R-CVP N = 162 |  | CVP N = 160
Median PFS (years) [p < 0.0001, two-sided stratified log-rank test.] | 2.4 |  | 1.4
Hazard ratio (95% CI) [Estimates of Cox regression stratified by center.] |  | 0.44 (0.29, 0.65)

NHL Study 5

An open-label, multicenter, randomized (1:1) study was conducted in 1,018 patients with previously untreated follicular NHL who achieved a response (CR or PR) to rituximab in combination with chemotherapy. Patients were randomized to rituximab as single-agent maintenance therapy, 375 mg/m^2 every 8 weeks for up to 12 doses or to observation. Rituximab was initiated at 8 weeks following completion of chemotherapy. The main outcome measure of the study was progression-free survival (PFS), defined as the time from randomization in the maintenance/observation phase to progression, relapse, or death, as determined by independent review.

Of the randomized patients, 40% were greater than or equal to 60 years of age, 70% had Stage IV disease, 96% had ECOG performance status (PS) 0–1, and 42% had FLIPI scores of 3–5. Prior to randomization to maintenance therapy, patients had received R-CHOP (75%), R-CVP (22%), or R-FCM (3%); 71% had a complete or unconfirmed complete response and 28% had a partial response.

PFS was longer in patients randomized to rituximab as single agent maintenance therapy (HR: 0.54, 95% CI: 0.42, 0.70; see Figure 1). The PFS results based on investigator assessment of progression were similar to those obtained by the independent review assessment.

Figure 1. Kaplan-Meier Plot of IRC Assessed PFS in NHL Study 5

NHL Study 6

A total of 322 patients with previously untreated low-grade, B-cell NHL who did not progress after 6 or 8 cycles of CVP chemotherapy were enrolled in an open-label, multicenter, randomized trial. Patients were randomized (1:1) to receive rituximab, 375 mg/m^2 intravenous infusion, once weekly for 4 doses every 6 months for up to 16 doses or no further therapeutic intervention. The main outcome measure of the study was progression-free survival defined as the time from randomization to progression, relapse, or death. Thirty-seven percent of the study population was greater than 60 years of age, 99% had Stage III or IV disease, and 63% had an IPI score greater than or equal to 2.

There was a reduction in the risk of progression, relapse, or death (hazard ratio estimate in the range of 0.36 to 0.49) for patients randomized to rituximab as compared to those who received no additional treatment.

14.3 Diffuse Large B-Cell NHL (DLBCL)

The safety and effectiveness of rituximab were evaluated in three randomized, active-controlled, open-label, multicenter studies with a collective enrollment of 1,854 patients. Patients with previously untreated diffuse large B-cell NHL received rituximab in combination with cyclophosphamide, doxorubicin, vincristine, and prednisone (CHOP) or other anthracycline-based chemotherapy regimens.

NHL Study 7

A total of 632 patients age greater than or equal to 60 years with DLBCL (including primary mediastinal B-cell lymphoma) were randomized in a 1:1 ratio to treatment with CHOP or R-CHOP. Patients received 6 or 8 cycles of CHOP, each cycle lasting 21 days. All patients in the R-CHOP arm received 4 doses of rituximab 375 mg/m^2 on Days –7 and –3 (prior to Cycle 1) and 48–72 hours prior to Cycles 3 and 5. Patients who received 8 cycles of CHOP also received rituximab prior to Cycle 7. The main outcome measure of the study was progression-free survival, defined as the time from randomization to the first of progression, relapse, or death. Responding patients underwent a second randomization to receive rituximab or no further therapy.

Among all enrolled patients, 62% had centrally confirmed DLBCL histology, 73% had Stage III–IV disease, 56% had IPI scores greater than or equal to 2, 86% had ECOG performance status of < 2, 57% had elevated LDH levels, and 30% had two or more extranodal disease sites involved. Efficacy results are presented in Table 11. These results reflect a statistical approach which allows for an evaluation of rituximab administered in the induction setting that excludes any potential impact of rituximab given after the second randomization.

Analysis of results after the second randomization in NHL Study 7 demonstrates that for patients randomized to R-CHOP, additional rituximab exposure beyond induction was not associated with further improvements in progression-free survival or overall survival.

NHL Study 8

A total of 399 patients with DLBCL, age greater than or equal to 60 years, were randomized in a 1:1 ratio to receive CHOP or R-CHOP. All patients received up to eight 3-week cycles of CHOP induction; patients in the R-CHOP arm received rituximab 375 mg/m^2 on Day 1 of each cycle. The main outcome measure of the study was event-free survival, defined as the time from randomization to relapse, progression, change in therapy, or death from any cause. Among all enrolled patients, 80% had Stage III or IV disease, 60% of patients had an age-adjusted IPI greater than or equal to 2, 80% had ECOG performance status scores less than 2, 66% had elevated LDH levels, and 52% had extranodal involvement in at least two sites. Efficacy results are presented in Table 11.

NHL Study 9

A total of 823 patients with DLBCL, aged 18–60 years, were randomized in a 1:1 ratio to receive an anthracycline-containing chemotherapy regimen alone or in combination with rituximab. The main outcome measure of the study was time to treatment failure, defined as time from randomization to the earliest of progressive disease, failure to achieve a complete response, relapse, or death. Among all enrolled patients, 28% had Stage III–IV disease, 100% had IPI scores of less than or equal to 1, 99% had ECOG performance status of less than 2, 29% had elevated LDH levels, 49% had bulky disease, and 34% had extranodal involvement. Efficacy results are presented in Table 11.

Table 11. Efficacy Results in NHL Studies 7, 8, and 9
 | Study 7 (n = 632) |  |  |  | Study 8 (n = 399) |  |  |  | Study 9 (n = 823)
 | R-CHOP |  | CHOP |  | R-CHOP |  | CHOP |  | R-Chemo |  | Chemo
Main outcome | Progression-free survival (years) |  |  |  | Event-free survival (years) |  |  |  | Time to treatment failure (years)
Median of main outcome measure | 3.1 |  | 1.6 |  | 2.9 |  | 1.1 |  | NE [NE = Not reliably estimable.] |  | NE
Hazard ratio [R-CHOP vs. CHOP.] |  | 0.69 [Significant at p < 0.05, 2-sided.] |  |  |  | 0.60 |  |  |  | 0.45
Overall survival at 2 years [Kaplan-Meier estimates.] | 74% |  | 63% |  | 69% |  | 58% |  | 95% |  | 86%
Hazard ratio |  | 0.72 |  |  |  | 0.68 |  |  |  | 0.40

In NHL Study 8, overall survival estimates at 5 years were 58% vs. 46% for R-CHOP and CHOP, respectively.

14.4 Ninety-Minute Infusions in Previously Untreated Follicular NHL and DLBCL

In NHL Study 10, a total of 363 patients with previously untreated follicular NHL (n = 113) or DLBCL (n = 250) were evaluated in a prospective, open-label, multi-center, single-arm trial for the safety of 90-minute rituximab infusions. Patients with follicular NHL received rituximab 375 mg/m^2 plus CVP chemotherapy. Patients with DLBCL received rituximab 375 mg/m^2 plus CHOP chemotherapy. Patients with clinically significant cardiovascular disease were excluded from the study. Patients were eligible for a 90-minute infusion at Cycle 2 if they did not experience a Grade 3-4 infusion-related adverse event with Cycle 1 and had a circulating lymphocyte count less than or equal to 5,000/mm^3 before Cycle 2. All patients were pre-medicated with acetaminophen and an antihistamine and received the glucocorticoid component of their chemotherapy prior to rituximab infusion. The main outcome measure was the development of Grade 3-4 infusion-related reactions on the day of, or day after, the 90-minute infusion at Cycle 2 [see Adverse Reactions (6.1)].

Eligible patients received their Cycle 2 rituximab infusion over 90 minutes as follows: 20% of the total dose given in the first 30 minutes and the remaining 80% of the total dose given over the next 60 minutes [see Dosage and Administration (2.1)]. Patients who tolerated the 90-minute rituximab infusion at Cycle 2 continued to receive subsequent rituximab infusions at the 90-minute infusion rate for the remainder of the treatment regimen (through Cycle 6 or Cycle 8).

The incidence of Grade 3-4 infusion-related reactions at Cycle 2 was 1.1% (95% CI [0.3%, 2.8%]) among all patients, 3.5% (95% CI [1.0%, 8.8%]) for those patients treated with R-CVP, and 0.0% (95% CI [0.0%, 1.5%]) for those patients treated with R-CHOP. For Cycles 2-8, the incidence of Grade 3-4 infusion-related reactions was 2.8% (95% CI [1.3%, 5.0%]). No acute fatal infusion-related reactions were observed.

14.5 Chronic Lymphocytic Leukemia (CLL)

The safety and effectiveness of rituximab were evaluated in two randomized (1:1) multicenter open-label studies comparing FC alone or in combination with rituximab for up to 6 cycles in patients with previously untreated CLL [CLL Study 1 (n = 817)] or previously treated CLL [CLL Study 2 (n = 552)]. Patients received fludarabine 25 mg/m^2/day and cyclophosphamide 250 mg/m^2/day on days 1, 2 and 3 of each cycle, with or without rituximab. In both studies, seventy-one percent of CLL patients received 6 cycles and 90% received at least 3 cycles of rituximab-based therapy.

In CLL Study 1, 30% of patients were 65 years or older, 31% were Binet stage C, 45% had B symptoms, more than 99% had ECOG performance status (PS) 0–1, 74% were male, and 100% were White. In CLL Study 2, 44% of patients were 65 years or older, 28% had B symptoms, 82% received a prior alkylating drug, 18% received prior fludarabine, 100% had ECOG PS 0–1, 67% were male and 98% were White.

The main outcome measure in both studies was progression-free survival (PFS), defined as the time from randomization to progression, relapse, or death, as determined by investigators (CLL Study 1) or an independent review committee (CLL Study 2). The investigator assessed results in CLL Study 2 were supportive of those obtained by the independent review committee. Efficacy results are presented in Table 12.

Table 12. Efficacy Results in CLL Studies 1 and 2
 | Study 1 [As defined in 1996 National Cancer Institute Working Group guidelines.] (Previously untreated) |  |  |  | Study 2 (Previously treated)
 | R-FC N = 408 |  | FC N = 409 |  | R-FC N = 276 |  | FC N = 276
Median PFS (months) | 39.8 |  | 31.5 |  | 26.7 |  | 21.7
Hazard ratio (95% CI) | 0.56 (0.43, 0.71) |  |  |  | 0.76 (0.6, 0.96)
P value (Log-Rank test) | < 0.01 |  |  |  | 0.02
Response rate (95% CI) | 86% (82, 89) |  | 73% (68, 77) |  | 54% (48, 60) |  | 45% (37, 51)

Across both studies, 243 of 676 rituximab-treated patients (36%) were 65 years of age or older and 100 rituximab-treated patients (15%) were 70 years of age or older. The results of exploratory subset analyses in elderly patients are presented in Table 13.

Table 13. Efficacy Results in CLL Studies 1 and 2 in Subgroups Defined by Age [From exploratory analyses.]
 | Study 1 |  | Study 2
Age subgroup | Number of Patients | Hazard Ratio for PFS (95% CI) | Number of Patients | Hazard Ratio for PFS (95% CI)
Age less than 65 yrs | 572 | 0.52 (0.39, 0.70) | 313 | 0.61 (0.45, 0.84)
Age greater than or equal to 65 yrs | 245 | 0.62 (0.39, 0.99) | 233 | 0.99 (0.70, 1.40)
Age less than 70 yrs | 736 | 0.51 (0.39, 0.67) | 438 | 0.67 (0.51, 0.87)
Age greater than or equal to 70 yrs | 81 | 1.17 (0.51, 2.66) | 108 | 1.22 (0.73, 2.04)

14.6 Rheumatoid Arthritis (RA)

Reducing the Signs and Symptoms: Initial and Re-Treatment Courses

The efficacy and safety of rituximab were evaluated in two randomized, double-blind, placebo-controlled studies of adult patients with moderately to severely active RA who had a prior inadequate response to at least one TNF inhibitor. Patients were 18 years of age or older, diagnosed with active RA according to American College of Rheumatology (ACR) criteria, and had at least 8 swollen and 8 tender joints.

In RA Study 1 (NCT00468546), patients were randomized to receive either rituximab 2×1,000 mg+MTX or placebo +MTX for 24 weeks. Further courses of rituximab 2×1,000 mg+MTX were administered in an open label extension study at a frequency determined by clinical evaluation, but no sooner than 16 weeks after the preceding course of rituximab. In addition to the intravenous premedication, glucocorticoids were administered orally on a tapering schedule from baseline through Day 14. The proportions of patients achieving ACR 20, 50, and 70 responses at Week 24 of the placebo-controlled period are shown in Table 14.

In RA Study 2 (NCT00266227), all patients received the first course of rituximab 2 × 1,000 mg + MTX. Patients who experienced ongoing disease activity were randomized to receive a second course of either rituximab 2 × 1,000 mg + MTX or placebo + MTX, the majority between Weeks 24–28. The proportions of patients achieving ACR 20, 50, and 70 responses at Week 24, before the re-treatment course, and at Week 48, after retreatment, are shown in Table 14.

Table 14. ACR Responses in RA Study 1 and RA Study 2 (Percent of Patients) (Modified Intent-to-Treat Population)
Inadequate Response to TNF Antagonists
 | Study 1 24 Week Placebo-Controlled (Week 24) |  |  |  | Study 2 Placebo-Controlled Retreatment (Week 24 and Week 48)
Response | Placebo + MTX n = 201 | Rituximab + MTX n = 298 | Treatment Difference (Rituximab – Placebo) [For RA Study 1, weighted difference stratified by region (US, rest of the world) and Rheumatoid Factor (RF) status (positive greater than 20 IU/mL, negative < 20 IU/mL) at baseline; For RA Study 2, weighted difference stratified by RF status at baseline and greater than or equal to 20% improvement from baseline in both SJC and TJC at Week 24 (Yes/No).] (95% CI) |  | Response | Placebo + MTX Retreatment n = 157 | Rituximab + MTX Retreatment n = 318 | Treatment Difference (Rituximab – Placebo) [In RA Study 2, all patients received a first course of rituximab 2 × 1,000 mg. Patients who experienced ongoing disease activity were randomized to receive a second course of either rituximab 2 × 1,000 mg + MTX or placebo + MTX at or after Week 24.] , [Since all patients received a first course of rituximab, no comparison between placebo + MTX and rituximab + MTX is made at Week 24.] , (95% CI)
ACR20 |  |  |  |  | ACR20
Week 24 | 18% | 51% | 33% (26%, 41%) |  | Week 24 | 48% | 45% | NA
 |  |  |  |  | Week 48 | 45% | 54% | 11% (2%, 20%)
ACR50 |  |  |  |  | ACR50
Week 24 | 5% | 27% | 21% (15%, 27%) |  | Week 24 | 27% | 21% | NA
 |  |  |  |  | Week 48 | 26% | 29% | 4% (-4%, 13%)
ACR70 |  |  |  |  | ACR70
Week 24 | 1% | 12% | 11% (7%, 15%) |  | Week 24 | 11% | 8% | NA
 |  |  |  |  | Week 48 | 13% | 14% | 1% (-5%, 8%)

Improvement was also noted for all components of ACR response following treatment with rituximab, as shown in Table 15.

Table 15. Components of ACR Response at Week 24 in RA Study 1 (Modified Intent-to-Treat Population)
Inadequate Response to TNF Antagonists
Parameter (median) | Placebo + MTX (n = 201) |  | Rituximab + MTX (n = 298)
Parameter (median) | Baseline | Wk 24 | Baseline | Wk 24
Tender Joint Count | 31.0 | 27.0 | 33.0 | 13.0
Swollen Joint Count | 20.0 | 19.0 | 21.0 | 9.5
Physician Global Assessment [Visual Analogue Scale: 0 = best, 100 = worst.] | 71.0 | 69.0 | 71.0 | 36.0
Patient Global Assessment | 73.0 | 68.0 | 71.0 | 41.0
Pain | 68.0 | 68.0 | 67.0 | 38.5
Disability Index (HAQ) [Disability Index of the Health Assessment Questionnaire: 0 = best, 3 = worst.] | 2.0 | 1.9 | 1.9 | 1.5
CRP (mg/dL) | 2.4 | 2.5 | 2.6 | 0.9

The time course of ACR 20 response for RA Study 1 is shown in Figure 2. Although both treatment groups received a brief course of intravenous and oral glucocorticoids, resulting in similar benefits at Week 4, higher ACR 20 responses were observed for the rituximab group by Week 8. A similar proportion of patients achieved these responses through Week 24 after a single course of treatment (2 infusions) with rituximab. Similar patterns were demonstrated for ACR 50 and 70 responses.

Figure 2. Percent of Patients Achieving ACR 20 Response by Visit [The same patients may not have responded at each time point.] RA Study 1 (Inadequate Response to TNF Antagonists)

Radiographic Response

In RA Study 1, structural joint damage was assessed radiographically and expressed as changes in Genant-modified Total Sharp Score (TSS) and its components, the erosion score (ES) and the joint space narrowing (JSN) score. Rituximab + MTX slowed the progression of structural damage compared to placebo + MTX after 1 year as shown in Table 16.

Table 16. Mean Radiographic Change from Baseline to 104 Weeks in RA Study 1
Inadequate Response to TNF Antagonists
Parameter | Rituximab 2 × 1,000 mg + MTX [Patients received up to 2 years of treatment with rituximab + MTX.] | Placebo + MTX [Patients receiving placebo + MTX. Patients receiving placebo + MTX could have received retreatment with rituximab + MTX from Week 16 onward.] | Treatment Difference (Placebo – Rituximab) | 95% CI
Change during First Year
TSS | 0.66 | 1.77 | 1.11 | (0.47, 1.75)
ES | 0.44 | 1.19 | 0.75 | (0.32, 1.19)
JSN Score | 0.22 | 0.58 | 0.36 | (0.10, 0.62)
Change during Second Year [Based on radiographic scoring following 104 weeks of observation.]
TSS | 0.48 | 1.04 | — | —
ES | 0.28 | 0.62 | — | —
JSN Score | 0.20 | 0.42 | — | —

In RA Study 1 and its open-label extension, 70% of patients initially randomized to rituximab + MTX and 72% of patients initially randomized to placebo + MTX were evaluated radiographically at Year 2. As shown in Table 16, progression of structural damage in rituximab + MTX patients was further reduced in the second year of treatment.

Following 2 years of treatment with rituximab + MTX, 57% of patients had no progression of structural damage. During the first year, 60% of rituximab + MTX treated patients had no progression, defined as a change in TSS of zero or less compared to baseline, compared to 46% of placebo + MTX treated patients. In their second year of treatment with rituximab + MTX, more patients had no progression than in the first year (68% vs. 60%), and 87% of the rituximab + MTX treated patients who had no progression in the first year also had no progression in the second year.

Lesser Efficacy of 500 Vs. 1,000 mg Treatment Courses for Radiographic Outcomes

RA Study 3 (NCT00299104) is a randomized, double-blind, placebo-controlled study which evaluated the effect of placebo + MTX compared to rituximab 2 × 500 mg + MTX and rituximab 2 × 1,000 mg + MTX treatment courses in MTX-naïve RA patients with moderately to severely active disease. Patients received a first course of two infusions of rituximab or placebo on Days 1 and 15. MTX was initiated at 7.5 mg/week and escalated up to 20 mg/week by Week 8 in all three treatment arms. After a minimum of 24 weeks, patients with ongoing disease activity were eligible to receive re-treatment with additional courses of their assigned treatment. After one year of treatment, the proportion of patients achieving ACR 20/50/70 responses were similar in both rituximab dose groups and were higher than in the placebo group. However, with respect to radiographic scores, only the rituximab 1,000 mg treatment group demonstrated a statistically significant reduction in TSS: a change of 0.36 units compared to 1.08 units for the placebo group, a 67% reduction.

Physical Function Response

RA Study 4 (NCT00299130) is a randomized, double-blind, placebo-controlled study in adult RA patients with moderately to severely active disease with inadequate response to MTX. Patients were randomized to receive an initial course of rituximab 500 mg, rituximab 1,000 mg, or placebo in addition to background MTX.

Physical function was assessed at Weeks 24 and 48 using the Health Assessment Questionnaire Disability Index (HAQ-DI). From baseline to Week 24, a greater proportion of rituximab-treated patients had an improvement in HAQ-DI of at least 0.22 (a minimal clinically important difference) and a greater mean HAQ-DI improvement compared to placebo, as shown in Table 17. HAQ-DI results for the rituximab 500 mg treatment group were similar to the rituximab 1,000 mg treatment group; however radiographic responses were not assessed (see Dosing Precaution in the Radiographic Responses section above). These improvements were maintained at 48 weeks.

Table 17. Improvement from Baseline in Health Assessment Questionnaire Disability Index (HAQ-DI) at Week 24 in RA Study 4
 | Placebo + MTX n = 172 | Rituximab 2 × 1,000 mg + MTX n = 170 | Treatment Difference (Rituximab – Placebo) [Adjusted difference stratified by region (US, rest of the world) and rheumatoid factor (RF) status (positive greater than or equal to 20 IU/mL, negative less than 20 IU/mL) at baseline.] (95% CI)
Mean Improvement from Baseline | 0.19 | 0.42 | 0.23 (0.11, 0.34)
Percent of patients with "Improved" score (Change from Baseline greater than or equal to MCID) [Minimal Clinically Important Difference: MCID for HAQ = 0.22.] | 48% | 58% | 11% (0%, 21%)

14.7 Granulomatosis with Polyangiitis (GPA) (Wegener's Granulomatosis) and Microscopic Polyangiitis (MPA)

Induction Treatment of Adult Patients with Active Disease (GPA/MPA Study 1)

A total of 197 patients with active, severe GPA and MPA (two forms of ANCA Associated Vasculitides) were treated in a randomized, double-blind, active-controlled multicenter, non-inferiority study, conducted in two phases – a 6-month remission induction phase and a 12-month remission maintenance phase. Patients were 15 years of age or older, diagnosed with GPA (75% of patients) or MPA (24% of patients) according to the Chapel Hill Consensus conference criteria (1% of the patients had unknown vasculitis type). All patients had active disease, with a Birmingham Vasculitis Activity Score for Granulomatosis with Polyangiitis (BVAS/GPA) greater than or equal to 3, and their disease was severe, with at least one major item on the BVAS/GPA. Ninety-six (49%) of patients had new disease and 101 (51%) of patients had relapsing disease.

Patients in both arms received 1,000 mg of pulse intravenous methylprednisolone per day for 1 to 3 days within 14 days prior to initial infusion. Patients were randomized in a 1:1 ratio to receive either rituximab 375 mg/m^2 once weekly for 4 weeks or oral cyclophosphamide 2 mg/kg daily for 3 to 6 months in the remission induction phase. Patients were pre-medicated with antihistamine and acetaminophen prior to rituximab infusion. Following intravenous corticosteroid administration, all patients received oral prednisone (1 mg/kg/day, not exceeding 80 mg/day) with pre-specified tapering. Once remission was achieved or at the end of the 6-month remission induction period, the cyclophosphamide group received azathioprine to maintain remission. The rituximab group did not receive additional therapy to maintain remission. The main outcome measure for both GPA and MPA patients was achievement of complete remission at 6 months defined as a BVAS/GPA of 0, and off glucocorticoid therapy. The pre-specified non-inferiority margin was a treatment difference of 20%. As shown in Table 18, the study demonstrated non-inferiority of rituximab to cyclophosphamide for complete remission at 6 months.

Table 18. Percentage of Patients with GPA/ MPA Who Achieved Complete Remission at 6 Months (Intent-to-Treat Population)
 | Rituximab (n = 99) | Cyclophosphamide (n = 98) | Treatment Difference (Rituximab – Cyclophosphamide)
Rate 95.1% CI [The 95.1% confidence level reflects an additional 0.001 alpha to account for an interim efficacy analysis.] | 64% (54%, 73%) | 53% (43%, 63%) | 11% (-3%, 24%) [Non-inferiority was demonstrated because the lower bound was higher than the prespecified non-inferiority margin (-3% greater than -20%).]

Complete Remission (CR) at 12 and 18 months

In the rituximab group, 44% of patients achieved CR at 6 and 12 months, and 38% of patients achieved CR at 6, 12, and 18 months. In patients treated with cyclophosphamide (followed by azathioprine for maintenance of CR), 38% of patients achieved CR at 6 and 12 months, and 31% of patients achieved CR at 6, 12, and 18 months.

Retreatment of Flares with Rituximab

Based upon investigator judgment, 15 patients received a second course of rituximab therapy for treatment of relapse of disease activity which occurred between 8 and 17 months after the induction treatment course of rituximab.

Follow up Treatment of Adult Patients with GPA/MPA who have achieved disease control with other Immunosuppressant (GPA/MPA Study 2)

A total of 115 patients (86 with GPA, 24 with MPA, and 5 with renal-limited ANCA-associated vasculitis) in disease remission were randomized to receive azathioprine (58 patients) or non-U.S.-licensed rituximab (57 patients) in this open-label, prospective, multi-center, randomized, active-controlled study. Eligible patients were 21 years and older and had either newly diagnosed (80%) or relapsing disease (20%). A majority of the patients were ANCA-positive. Remission of active disease was achieved using a combination of glucocorticoids and cyclophosphamide. Within a maximum of 1 month after the last cyclophosphamide dose, eligible patients (based on BVAS of 0), were randomized in a 1:1 ratio to receive either non-U.S.-licensed rituximab or azathioprine.

The non-U.S.-licensed rituximab was administered as two 500 mg intravenous infusions separated by two weeks (on Day 1 and Day 15) followed by a 500 mg intravenous infusion every 6 months for 18 months. Azathioprine was administered orally at a dose of 2 mg/kg/day for 12 months, then 1.5 mg/kg/day for 6 months, and finally 1 mg/kg/day for 4 months; treatment was discontinued after 22 months. Prednisone treatment was tapered and then kept at a low dose (approximately 5 mg per day) for at least 18 months after randomization. Prednisone dose tapering and the decision to stop prednisone treatment after Month 18 were left at the investigator's discretion.

Planned follow-up was until Month 28 (10 or 6 months, respectively, after the last non-U.S.-licensed rituximab infusion or azathioprine dose). The primary endpoint was the occurrence of major relapse (defined by the reappearance of clinical and/or laboratory signs of vasculitis activity that could lead to organ failure or damage, or could be life threatening) through Month 28.

By Month 28, major relapse occurred in 3 patients (5%) in the non-U.S.-licensed rituximab group and 17 patients (29%) in the azathioprine group.

The observed cumulative incidence rate of first major relapse during the 28 months was lower in patients on non-U.S.-licensed rituximab relative to azathioprine (Figure 3).

Figure 3. Cumulative Incidence Over Time of First Major Relapse in Patients with GPA/MPA

Patients were censored at the last follow-up dates if they had no event.

14.8 Pemphigus Vulgaris (PV)

PV Study 1 (NCT00784589)

Non-U.S.-licensed rituximab in combination with short-term prednisone was compared to prednisone monotherapy as first-line treatment in 90 newly diagnosed adult patients with moderate to severe pemphigus (74 Pemphigus Vulgaris [PV] and 16 Pemphigus Foliaceus [PF]) in this randomized, open-label, controlled, multicenter study (PV Study 1). Patients were between 19 and 79 years of age and had not received prior therapies for pemphigus. In the PV population, 5 (13%) patients in the group treated with non-U.S.-licensed rituximab and 3 (8%) patients in the prednisone group had moderate disease and 33 (87%) patients in the group treated with non-U.S.-licensed rituximab and 33 (92%) patients in the prednisone group had severe disease according to disease severity defined by Harman's criteria.

Patients were stratified by baseline disease severity (moderate or severe) and randomized 1:1 to receive either the non-U.S.-licensed rituximab and short-term prednisone or long-term prednisone monotherapy. Patients were pre-medicated with antihistamine, acetaminophen and methylprednisolone prior to infusion of the non-U.S.-licensed rituximab. Patients randomized to the group treated with non-U.S.-licensed rituximab received an initial intravenous infusion of 1,000 mg non-U.S.-licensed rituximab on Study Day 1 in combination with a short-term regimen of 0.5 mg/kg/day oral prednisone tapered off over 3 months if they had moderate disease or 1 mg/kg/day oral prednisone tapered off over 6 months if they had severe disease. All patients received a second intravenous infusion of 1,000 mg non-U.S.-licensed rituximab on Study Day 15. Maintenance infusions of 500 mg non-U.S.-licensed rituximab were administered at Months 12 and 18. Patients randomized to the prednisone monotherapy group received an initial 1 mg/kg/day oral prednisone tapered off over 12 months if they had moderate disease or 1.5 mg/kg/day oral prednisone tapered off over 18 months if they had severe disease. Patients in the group treated with non-U.S.-licensed rituximab who relapsed could receive an additional infusion of 1,000 mg non-U.S.-licensed rituximab in combination with reintroduced or escalated prednisone dose. Maintenance and relapse infusions were administered no sooner than 16 weeks following the previous infusion.

The primary endpoint for the study was complete remission (complete epithelialization and absence of new and/or established lesions) at Month 24 without the use of prednisone therapy for 2 months or more (CRoff for greater than or equal to 2 months).

The results of the trial are presented in Table 19.

Table 19. Percentage of Pemphigus Patients in Complete Remission Off Corticosteroid Therapy for Two Months or More (CRoff greater than or equal to 2 months) at Month 24, PV Study 1 (Intent-to-Treat Population)
 | Non-U.S.-licensed Rituximab + Short-term Prednisone N = 46 | Prednisone N = 44
Number of responders (response rate [%]) | 41 (89%) | 15 (34%)
PV patients | 34/38 (90%) | 10/36 (28%)
PF patients | 7/8 (88%) | 5/8 (63%)

PV Study 2 (NCT02383589)

In a randomized, double-blind, double-dummy, active-comparator, multicenter study, the efficacy and safety of rituximab compared to mycophenolate mofetil (MMF) were evaluated in patients with moderate-to-severe PV receiving 60-120 mg/day oral prednisone or equivalent (1.0-1.5 mg/kg/day) at study entry and tapered to reach a dose of 60 or 80 mg/day by Day 1. Patients had a confirmed diagnosis of PV within the previous 24 months and evidence of moderate-to-severe disease defined as a total Pemphigus Disease Area Index (PDAI) activity score of greater than or equal to 15. The study consisted of a screening period of up to 28 days, a 52-week double-blind treatment period, and a 48-week safety follow up period.

One hundred and thirty-five patients were randomized to treatment with rituximab 1,000 mg administered on Day 1, Day 15, Week 24 and Week 26 or oral MMF 2 g/day (starting at 1 g/day on Day 1 and titrated to achieve a goal of 2 g/day by Week 2) for 52 weeks in combination with an initial dose of 60 or 80 mg oral prednisone with the aim of tapering to 0 mg/day by Week 24. Randomization was stratified by duration of PV (within the 1 year prior to screening or greater than 1 year) and geographical region. A dual-assessor approach was used during the study for efficacy and safety evaluations to prevent potential unblinding.

One hundred and twenty-five patients (excluding exploratory data from ten telemedicine patients) were analyzed for efficacy (Modified Intent-to-Treat Population). The primary efficacy endpoint for this study was the proportion of subjects achieving sustained complete remission defined as achieving healing of lesions with no new active lesions (i.e., PDAI activity score of 0) while on 0 mg/day prednisone or equivalent, and maintaining this response for at least 16 consecutive weeks, during the 52-week treatment period.

Secondary endpoints included cumulative oral corticosteroid dose and the total number of disease flares.

The results of the trial are presented in Table 20.

Table 20. Percentage of PV Patients Who Achieved Sustained Complete Remission Off Corticosteroid Therapy for 16 Weeks or More at Week 52 (Modified Intent-to-Treat Population)
 | Rituximab N = 62 | MMF N = 63 | Difference (95% CI)
Number of responders (response rate [%]) | 25 (40.3%) | 6 (9.5%) | 30.80% (14.70%, 45.15%)
MMF = Mycophenolate mofetil. CI = Confidence Interval.

Glucocorticoid exposure

The median (min, max) cumulative oral prednisone dose at Week 52 was 2,775 mg (450, 22,180) in the rituximab group compared to 4,005 mg (900, 19,920) in the MMF group. Topical corticosteroid use and pre-infusion IV methylprednisolone were not included in this analysis. Prior to each infusion, the rituximab group received IV methylprednisolone 100 mg and the MMF group received IV saline solution.

Disease flare

Disease flare was defined as an appearance of 3 or more new lesions a month that do not heal spontaneously within 1 week or by the extension of established lesions in a patient who has achieved disease control. The total number of disease flares was lower in patients treated with rituximab compared to MMF (6 vs. 44).

16 HOW SUPPLIED/STORAGE AND HANDLING

RIABNI (rituximab-arrx) injection is a sterile, clear to slightly opalescent, colorless to slightly yellow preservative free solution for intravenous use supplied as a carton containing one 100 mg/10 mL (10 mg/mL) single dose vial (NDC 55513-224-01, 55513-224-21) and a carton containing one 500 mg/50 mL (10 mg/mL) single dose vial (NDC 55513-326-01, 55513-326-21).

STORAGE AND HANDLING

Store RIABNI vials refrigerated at 2°C to 8°C (36°F to 46°F). Protect RIABNI vials from direct sunlight. Do not freeze or shake.

17 PATIENT COUNSELING INFORMATION

Advise the patient to read the FDA-approved patient labeling (Medication Guide).

Infusion-Related Reactions

Inform patients about the signs and symptoms of infusion-related reactions. Advise patients to contact their healthcare provider immediately to report symptoms of infusion-related reactions including urticaria, hypotension, angioedema, sudden cough, breathing problems, weakness, dizziness, palpitations, or chest pain [see Warnings and Precautions (5.1)].

Severe Mucocutaneous Reactions

Advise patients to contact their healthcare provider immediately for symptoms of severe mucocutaneous reactions, including painful sores or ulcers on the mouth, blisters, peeling skin, rash, and pustules [see Warnings and Precautions (5.2)].

Hepatitis B Virus Reactivation

Advise patients to contact their healthcare provider immediately for symptoms of hepatitis including worsening fatigue or yellow discoloration of skin or eyes [see Warnings and Precautions (5.3)].

Progressive Multifocal Leukoencephalopathy (PML)

Advise patients to contact their healthcare provider immediately for signs and symptoms of PML, including new or changes in neurological symptoms such as confusion, dizziness or loss of balance, difficulty talking or walking, decreased strength or weakness on one side of the body, or vision problems [see Warnings and Precautions (5.4)].

Tumor Lysis Syndrome (TLS)

Advise patients to contact their healthcare provider immediately for signs and symptoms of tumor lysis syndrome such as nausea, vomiting, diarrhea, and lethargy [see Warnings and Precautions (5.5)].

Infections

Advise patients to contact their healthcare provider immediately for signs and symptoms of infections including fever, cold symptoms (e.g., rhinorrhea or laryngitis), flu symptoms (e.g., cough, fatigue, body aches), earache or headache, dysuria, oral herpes simplex infection, and painful wounds with erythema and advise patients of the increased risk of infections during and after treatment with RIABNI [see Warnings and Precautions (5.6)].

Cardiovascular Adverse Reactions

Advise patients of the risk of cardiovascular adverse reactions, including ventricular fibrillation, myocardial infarction, and cardiogenic shock. Advise patients to contact their healthcare provider immediately to report chest pain and irregular heartbeats [see Warnings and Precautions (5.7)].

Renal Toxicity

Advise patients of the risk of renal toxicity. Inform patients of the need for healthcare providers to monitor kidney function [see Warnings and Precautions (5.8)].

Bowel Obstruction and Perforation

Advise patients to contact their healthcare provider immediately for signs and symptoms of bowel obstruction and perforation, including severe abdominal pain or repeated vomiting [see Warnings and Precautions (5.9)].

Embryo-Fetal Toxicity

Advise pregnant women of the potential risk to a fetus. Advise females of reproductive potential to inform their healthcare provider of a known or suspected pregnancy [see Warnings and Precautions (5.11), Use in Specific Populations (8.1)].

Advise females of reproductive potential to use effective contraception during treatment with RIABNI and for 12 months after the last dose [see Use in Specific Populations (8.3)].

Lactation

Advise women not to breastfeed during treatment with RIABNI and for 6 months after the last dose [see Use in Specific Populations (8.2)].

RIABNI® [rituximab-arrx]
Manufactured by:
Amgen, Inc.
One Amgen Center Drive
Thousand Oaks, CA 91320-1799
U.S. License Number 1080
AMGEN and RIABNI® are trademarks or licensed by Amgen, Inc., its subsidiaries or affiliates.
© 2020, 2022-2023, 2025 Amgen, Inc. All rights reserved.

1XXXXXX – v5

MEDICATION GUIDE
RIABNI® (re AB nee)
(rituximab-arrx)
injection

What is the most important information I should know about RIABNI?
RIABNI can cause serious side effects that can lead to death, including:

- Infusion-related reactions. Infusion-related reactions are very common side effects of RIABNI treatment. Serious infusion-related reactions can happen during your infusion or within 24 hours after your infusion of RIABNI. Your healthcare provider should give you medicines before your infusion of RIABNI to decrease your chance of having a severe infusion-related reaction.
  Tell your healthcare provider or get medical help right away if you get any of these symptoms during or after an infusion of RIABNI:

- hives (red itchy welts) or rash
- itching
- swelling of your lips, tongue, throat or face
- sudden cough

- shortness of breath, difficulty breathing, or wheezing
- weakness
- dizziness or feel faint
- palpitations (feel like your heart is racing or fluttering)
- chest pain

- Severe skin and mouth reactions. Tell your healthcare provider or get medical help right away if you get any of these symptoms at any time during your treatment with RIABNI:
  - painful sores or ulcers on your skin, lips or in your mouth
  - blisters
  - peeling skin
  - rash
  - pustules
- Hepatitis B virus (HBV) reactivation. Before you receive your RIABNI treatment, your healthcare provider will do blood tests to check for HBV infection. If you have had hepatitis B or are a carrier of hepatitis B virus, receiving RIABNI could cause the virus to become an active infection again. Hepatitis B reactivation may cause serious liver problems including liver failure, and death. You should not receive RIABNI if you have active hepatitis B liver disease. Your healthcare provider will monitor you for hepatitis B infection during and for several months after you stop receiving RIABNI.
  Tell your healthcare provider right away if you get worsening tiredness, or yellowing of your skin or white part of your eyes, during treatment with RIABNI.
- Progressive Multifocal Leukoencephalopathy (PML). PML is a rare, serious brain infection caused by a virus that can happen in people who receive RIABNI. People with weakened immune systems can get PML. PML can result in death or severe disability. There is no known treatment, prevention, or cure for PML.
  Tell your healthcare provider right away if you have any new or worsening symptoms or if anyone close to you notices these symptoms:

- confusion
- dizziness or loss of balance
- difficulty walking or talking

- decreased strength or weakness on one side of your body
- vision problems

See "What are the possible side effects of RIABNI?" for more information about side effects.

What is RIABNI?
RIABNI is a prescription medicine used to treat:

- Adults with Non-Hodgkin's Lymphoma (NHL): alone or with other chemotherapy medicines.
- Adults with Chronic Lymphocytic Leukemia (CLL): with the chemotherapy medicines fludarabine and cyclophosphamide.
- Adults with Rheumatoid Arthritis (RA): with another prescription medicine called methotrexate, to reduce the signs and symptoms of moderate to severe active RA in adults, after treatment with at least one other medicine called a Tumor Necrosis Factor (TNF) antagonist has been used and did not work well.
- Adults with Granulomatosis with Polyangiitis (GPA) (Wegener's Granulomatosis) and Microscopic Polyangiitis (MPA): with glucocorticoids, to treat GPA and MPA.
- Adults with Pemphigus Vulgaris (PV): to treat moderate to severe PV.

RIABNI is not indicated for treatment of children.

Before you receive RIABNI, tell your healthcare provider about all of your medical conditions, including if you:

- have had a severe reaction to RIABNI or another rituximab product.
- have a history of heart problems, irregular heart beat or chest pain.
- have lung or kidney problems.
- have an infection or weakened immune system.
- have or have had any severe infections including:

- Hepatitis B virus (HBV)
- Hepatitis C virus (HCV)
- Cytomegalovirus (CMV)
- Herpes simplex virus (HSV)

- Parvovirus B19
- Varicella zoster virus (chickenpox or shingles)
- West Nile Virus

- have had a recent vaccination or are scheduled to receive vaccinations. You should not receive certain vaccines before or during treatment with RIABNI.
- are pregnant or plan to become pregnant. Talk to your healthcare provider about the risks to your unborn baby if you receive RIABNI during pregnancy.
  Females who are able to become pregnant:
  - Your healthcare provider should do a pregnancy test to see if you are pregnant before starting RIABNI.
  - You should use effective birth control (contraception) during treatment with RIABNI and for 12 months after your last dose of RIABNI. Talk to your healthcare provider about effective birth control.
  - Tell your healthcare provider right away if you become pregnant or think that you are pregnant during treatment with RIABNI.
- are breastfeeding or plan to breastfeed. RIABNI may pass into your breast milk. Do not breastfeed during treatment and for 6 months after your last dose of RIABNI.

Tell your healthcare provider about all the medicines you take, including prescription and over-the-counter medicines, vitamins, and herbal supplements. Especially tell your healthcare provider if you take or have taken:

- a Tumor Necrosis Factor (TNF) inhibitor medicine.
- a Disease Modifying Anti-Rheumatic Drug (DMARD).

If you are not sure if your medicine is one listed above, ask your healthcare provider.

How will I receive RIABNI?

- RIABNI is given by infusion through your central catheter or through a needle placed in a vein (intravenous infusion), in your arm. Talk to your healthcare provider about how you will receive RIABNI.
- Your healthcare provider may prescribe medicines before each infusion of RIABNI to reduce infusion side effects such as fever and chills.
- Your healthcare provider should do blood test regularly to check for side effects to RIABNI.
- Before each RIABNI treatment, your healthcare provider or nurse will ask you questions about your general health. Tell your healthcare provider or nurse about any new symptoms.

What are the possible side effects of RIABNI?
RIABNI can cause serious side effects, including:

- See "What is the most important information I should know about RIABNI?"
- Tumor Lysis Syndrome (TLS). TLS is caused by the fast breakdown of cancer cells. TLS can cause you to have:
  - kidney failure and the need for dialysis treatment
  - abnormal heart rhythm
  TLS can happen within 12 to 24 hours after an infusion of RIABNI. Your healthcare provider may do blood tests to check you for TLS. Your healthcare provider may give you medicine to help prevent TLS. Tell your healthcare provider right away if you have any of the following signs or symptoms or TLS:

- nausea
- vomiting

- diarrhea
- lack of energy

- Serious infections. Serious infections can happen during and after treatment with RIABNI, and can lead to death. RIABNI can increase your risk of getting infections and can lower the ability of your immune system to fight infections. Types of serious infections that can happen with RIABNI include bacterial, fungal, and viral infections. After receiving RIABNI, some people have developed low levels of certain antibodies in their blood for a long period of time (longer than 11 months). Some of these people with low antibody levels developed infections. People with serious infections should not receive RIABNI. Tell your healthcare provider right away if you have any symptoms of infection:
  - fever
  - cold symptoms, such as runny nose or sore throat that do not go away
  - flu symptoms, such as cough, tiredness, and body aches
  - earache or headache
  - pain during urination
  - cold sores in the mouth or throat
  - cuts, scrapes or incisions that are red, warm, swollen or painful
- Heart problems. RIABNI may cause chest pain, irregular heartbeats, and heart attack. Your healthcare provider may monitor your heart during and after treatment with RIABNI if you have symptoms of heart problems or have a history of heart problems. Tell your healthcare provider right away if you have chest pain or irregular heartbeats during treatment with RIABNI.
- Kidney problems, especially if you are receiving RIABNI for NHL. RIABNI can cause severe kidney problems that lead to death. Your healthcare provider should do blood tests to check how well your kidneys are working.
- Stomach and serious bowel problems that can sometimes lead to death. Bowel problems, including blockage or tears in the bowel can happen if you receive RIABNI with chemotherapy medicines. Tell your healthcare provider right away if you have any severe stomach-area (abdomen) pain or repeated vomiting during treatment with RIABNI.

Your healthcare provider will stop treatment with RIABNI if you have severe, serious or life-threatening side effects.
The most common side effects of RIABNI include:

- infusion-related reactions (see "What is the most important information I should know about RIABNI?")
- infections (may include fever, chills)
- body aches
- tiredness
- nausea

In adults with GPA or MPA the most common side effects of RIABNI also include:

- low white and red blood cells
- swelling
- diarrhea
- muscle spasms

Other side effects with RIABNI include:

- aching joints during or within hours of receiving an infusion
- more frequent upper respiratory tract infection

These are not all of the possible side effects with RIABNI.
Call your doctor for medical advice about side effects. You may report side effects to FDA at 1-800-FDA-1088.

General information about the safe and effective use of RIABNI.
Medicines are sometimes prescribed for purposes other than those listed in a Medication Guide. You can ask your pharmacist or healthcare provider for information about RIABNI that is written for healthcare providers.

What are the ingredients in RIABNI?
Active ingredient: rituximab-arrx
Inactive ingredients: polysorbate 80, sodium chloride, sodium citrate dihydrate, and Water for Injection, USP.
Hydrochloric acid is used to adjust the buffer solution pH.
AMGEN
RIABNI® (rituxumab-arrx)
Manufactured by: Amgen, Inc., One Amgen Center Drive, Thousand Oaks, CA 91320-1799
U.S. License Number 1080
RIABNI® is a registered trademark of Amgen, Inc. © 2020, 2022-2023, 202X Amgen, Inc.
For more information, go to www.RIABNI.com or call 1-805-447-1000.
1XXXXXX – v4

This Medication Guide has been approved by the U.S. Food and Drug Administration.

Revised: 6/2025

PRINCIPAL DISPLAY PANEL - 100 mg/10 mL Vial Label

100
mg/10 mL

AMGEN®

RIABNI®
(rituximab-arrx)
Injection

NDC 55513-224-01
Single-dose Vial
Discard unused portion.

100 mg/10 mL (10 mg/mL)

For Intravenous Infusion After Dilution

Store refrigerated at 2°C to 8°C (36°F to 46°F).

Protect from direct sunlight. Do not freeze or shake.

Sterile Solution - No Preservative

ATTENTION: Enclosed Medication Guide is
required for each patient.

Contains 1 Single-dose Vial.

Rx Only

PRINCIPAL DISPLAY PANEL - 500 mg/50 mL Vial Label

500
mg/50 mL

AMGEN®

RIABNI®
(rituximab-arrx)
Injection

NDC 55513-326-01
Single-dose Vial
Discard unused portion.

500 mg/50 mL (10 mg/mL)

For Intravenous Infusion After Dilution

Store refrigerated at 2°C to 8°C (36°F to 46°F).

Protect from direct sunlight. Do not freeze or shake.

Sterile Solution - No Preservative

ATTENTION: Enclosed Medication Guide is required for each patient.

Contains 1 Single-dose Vial.

Rx Only